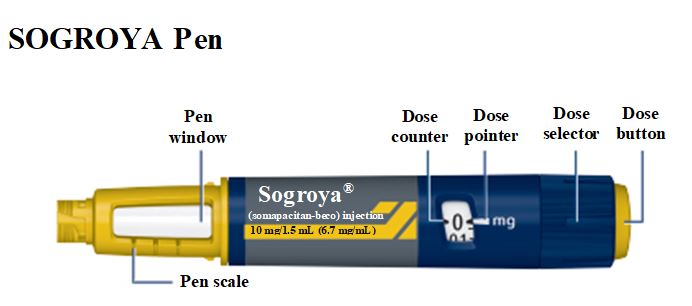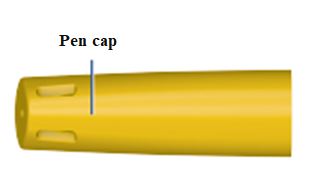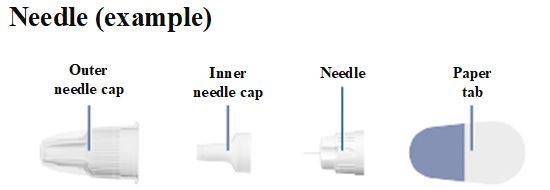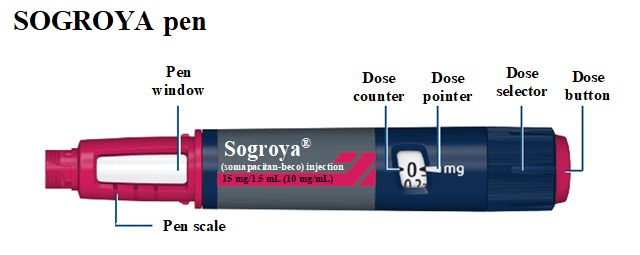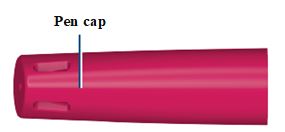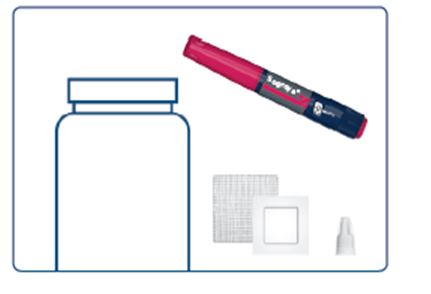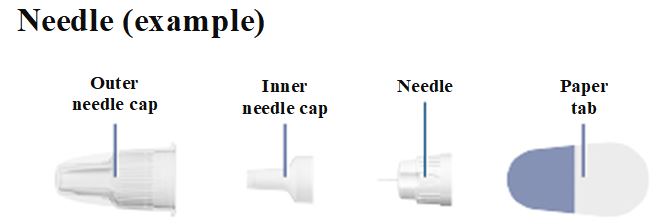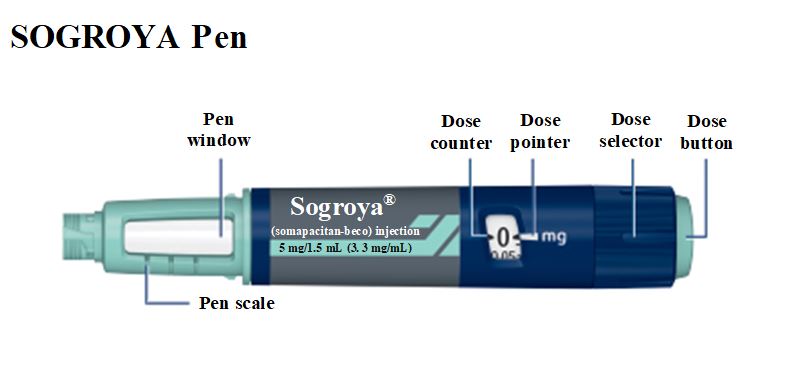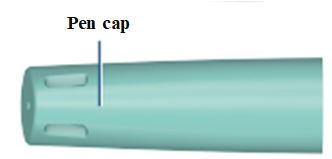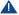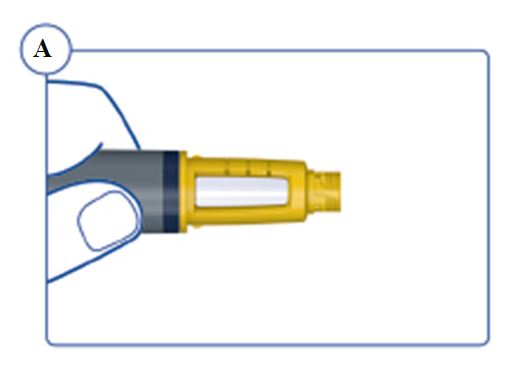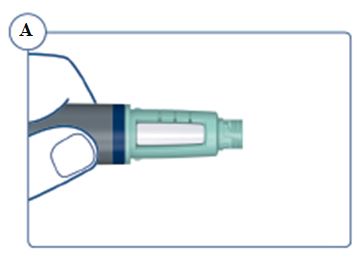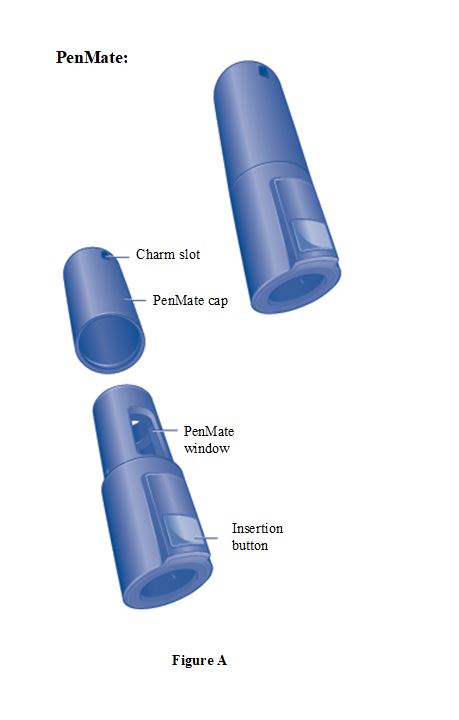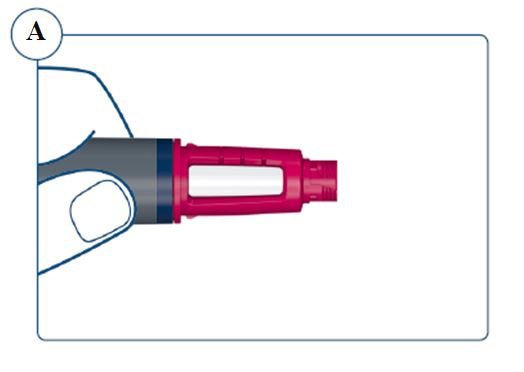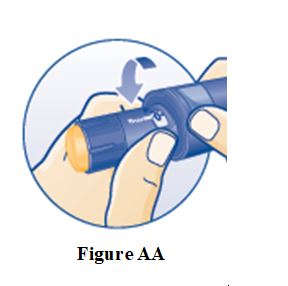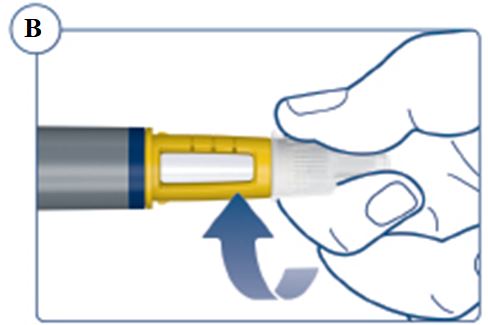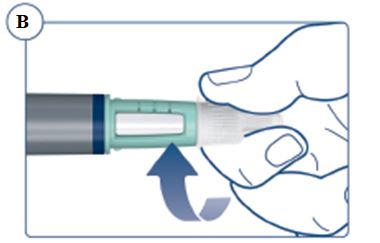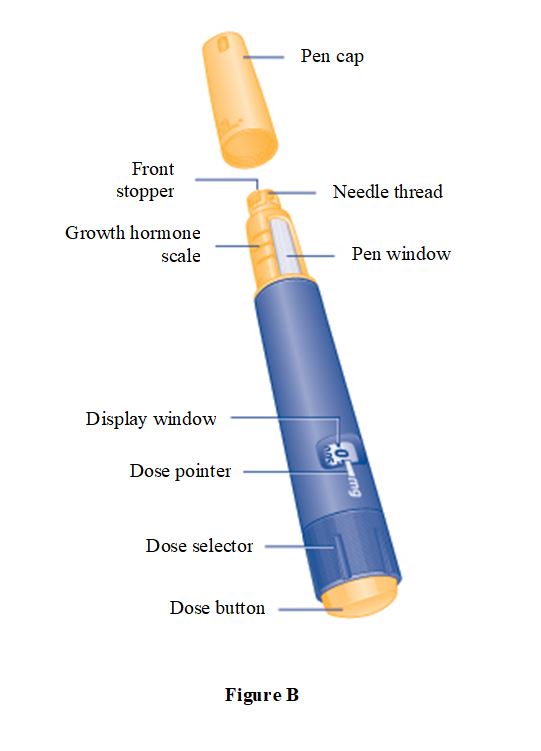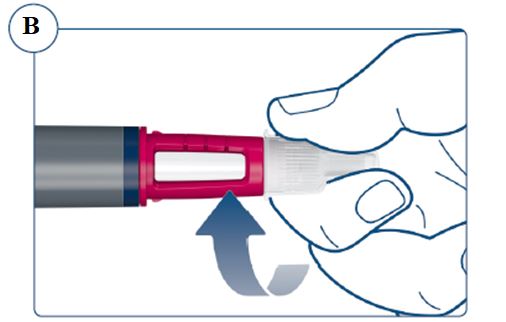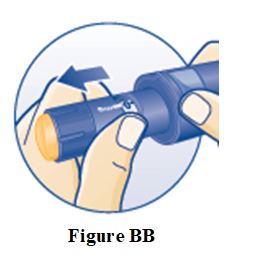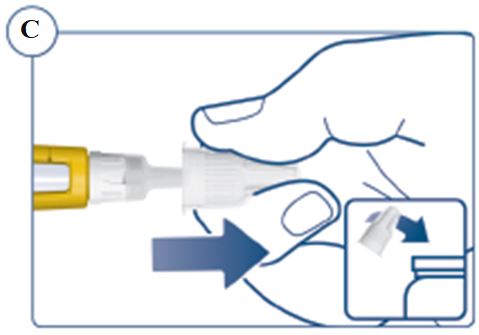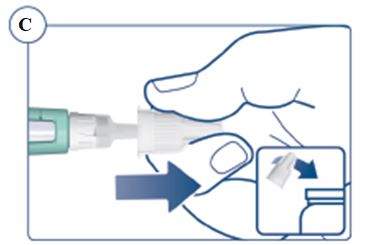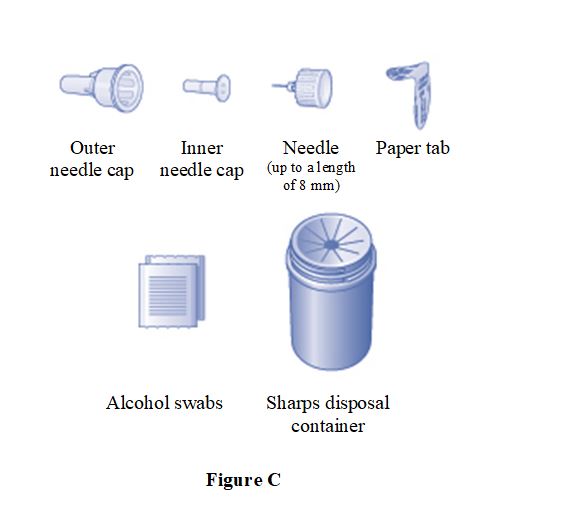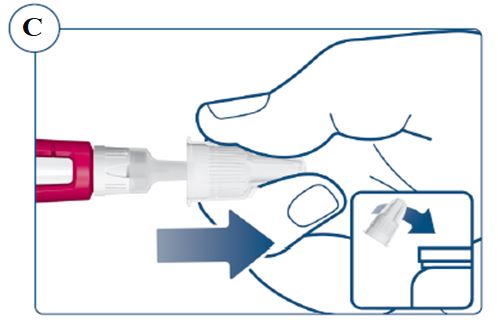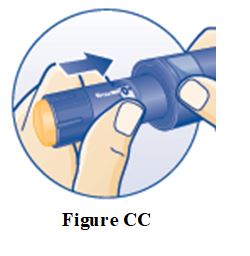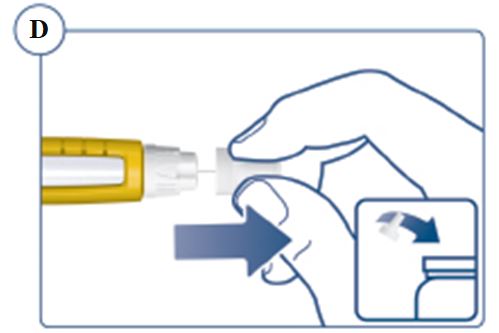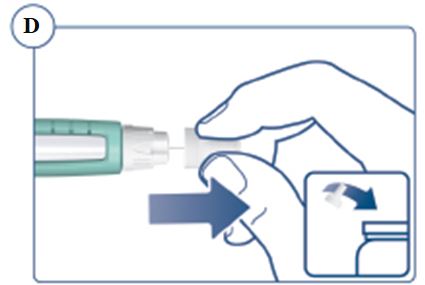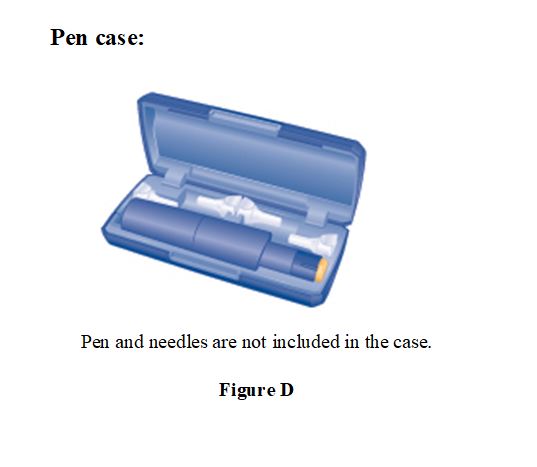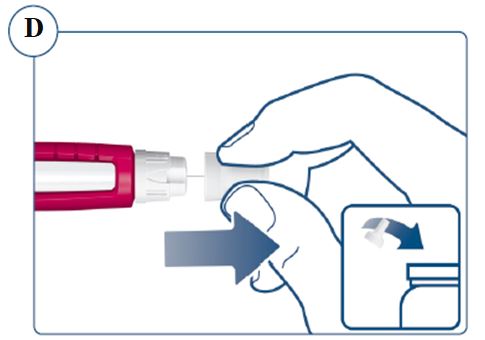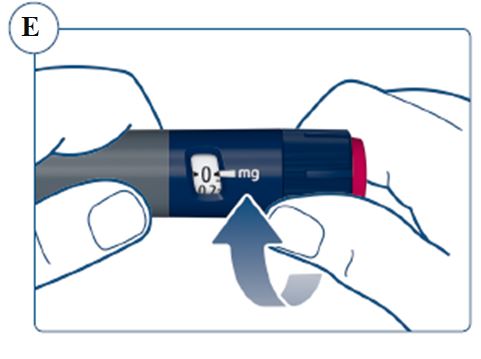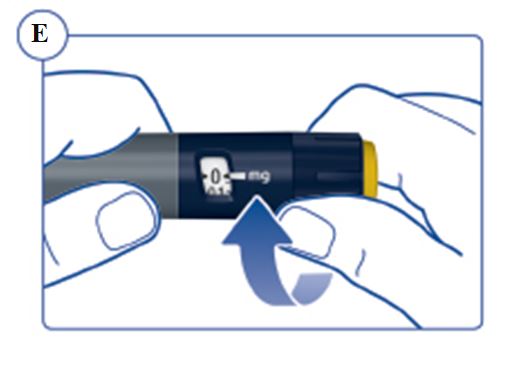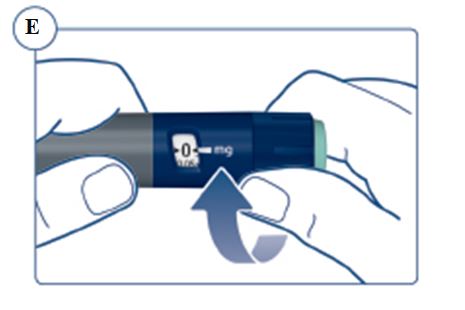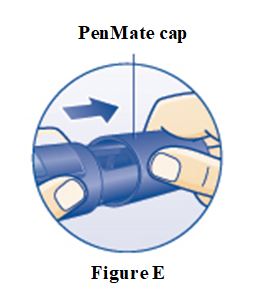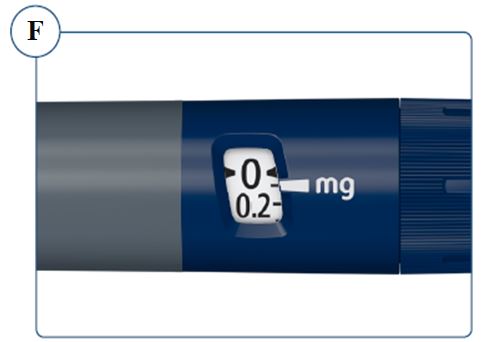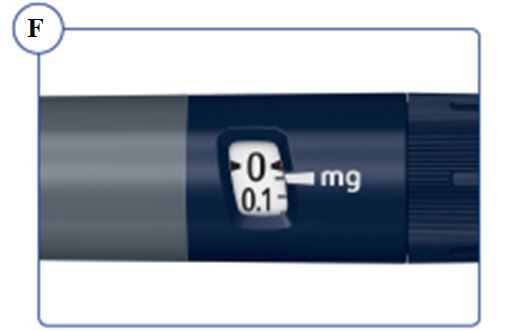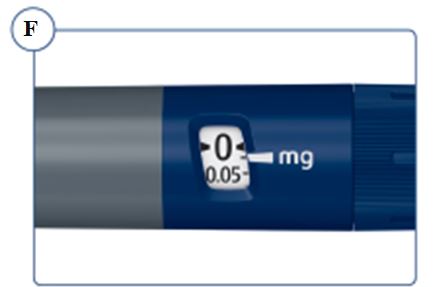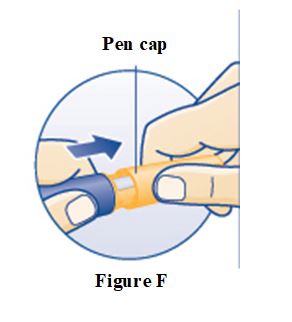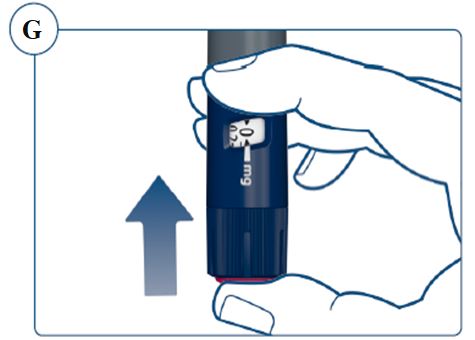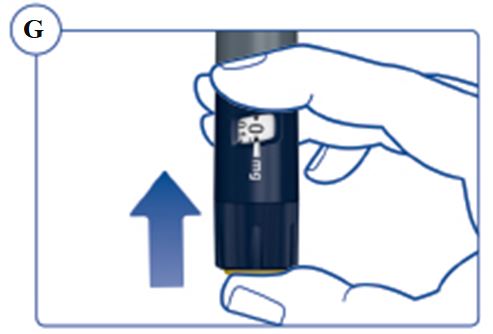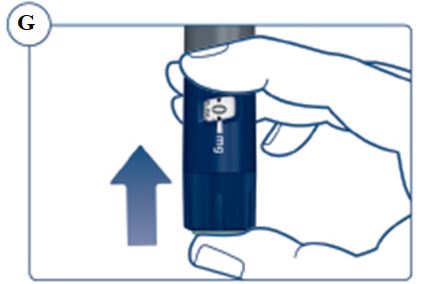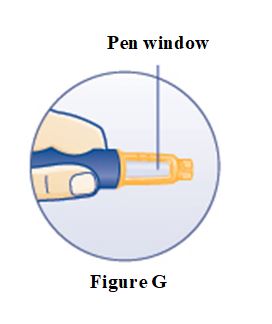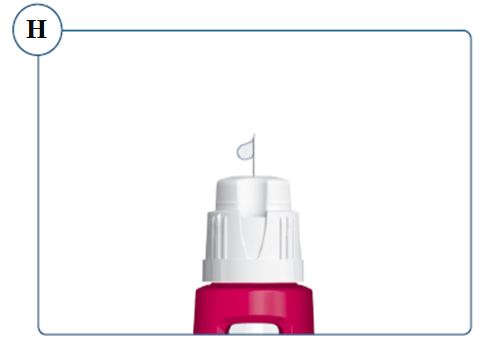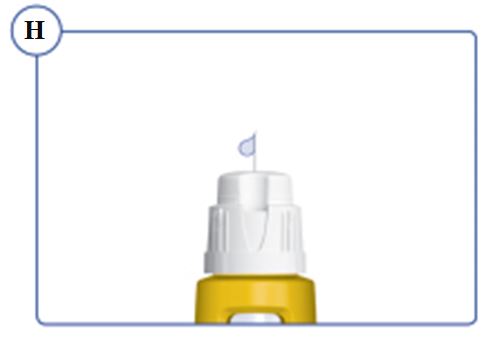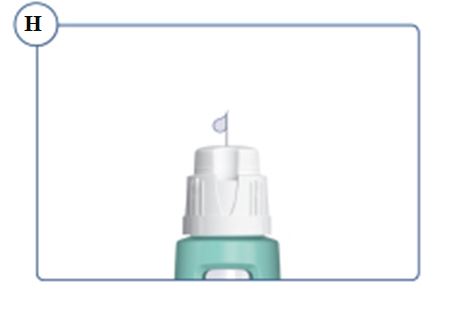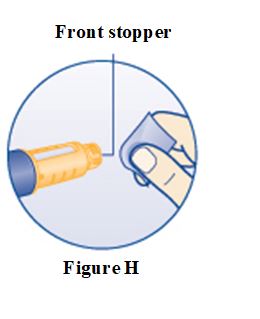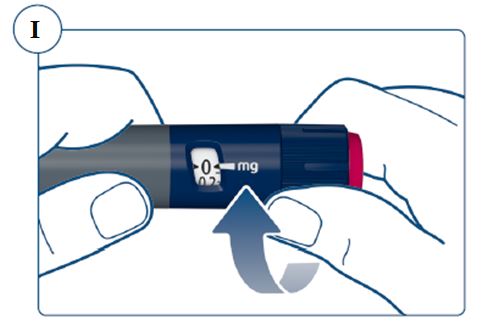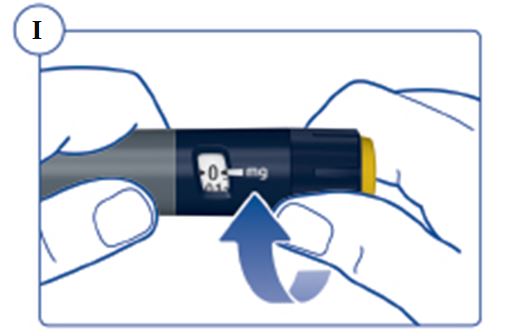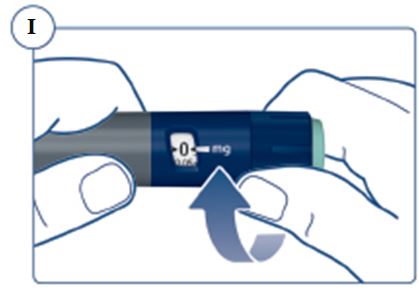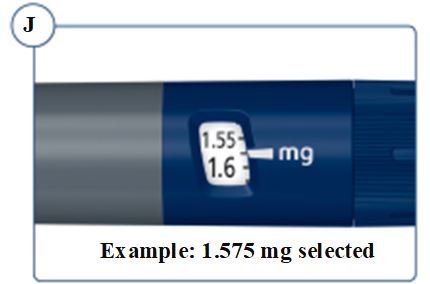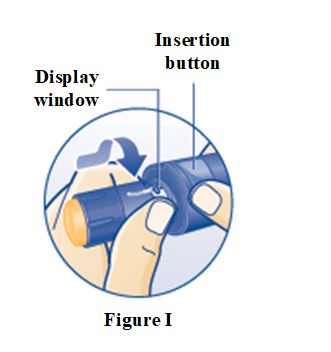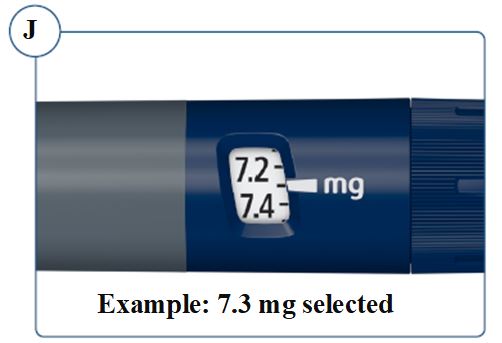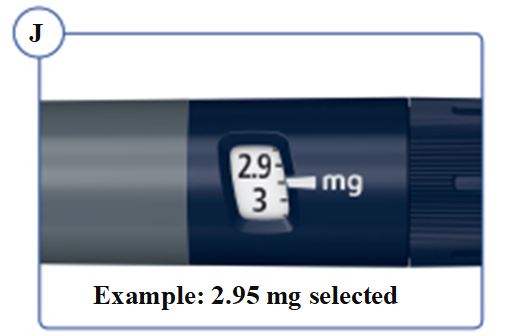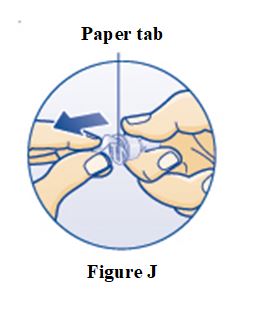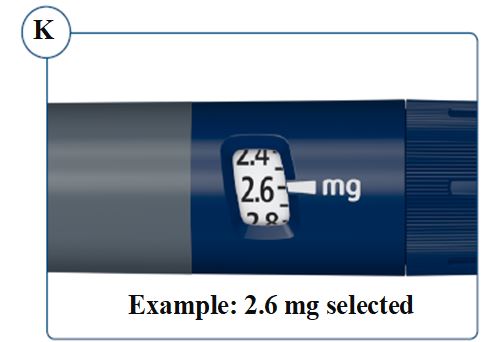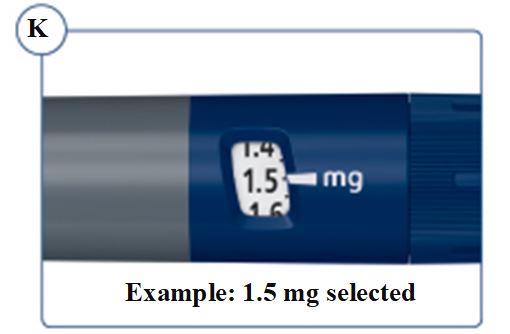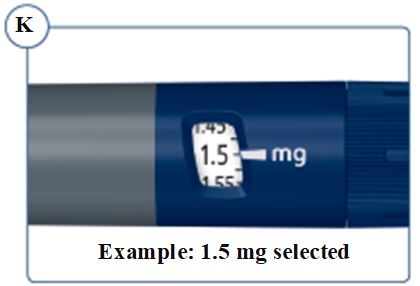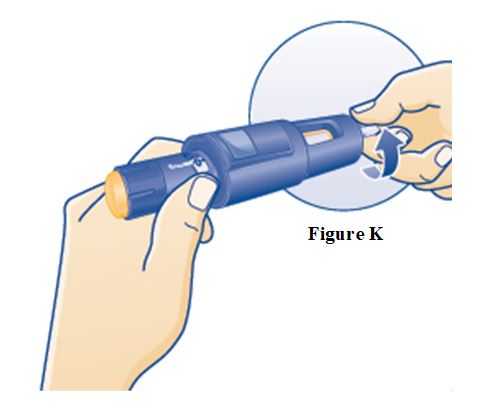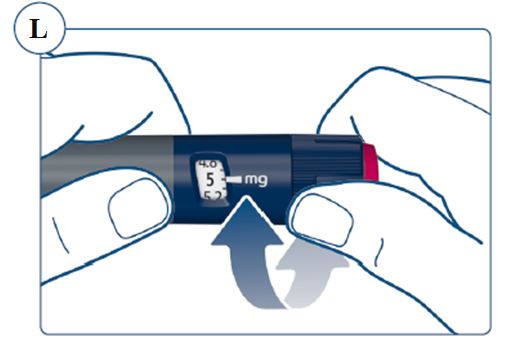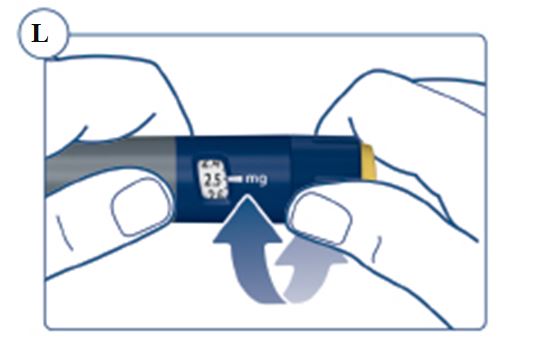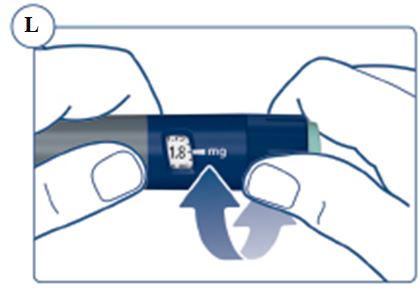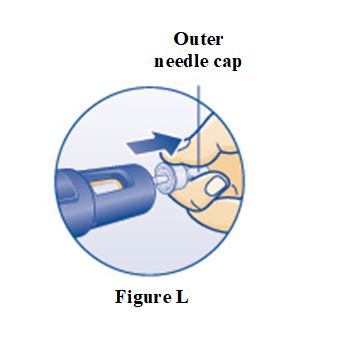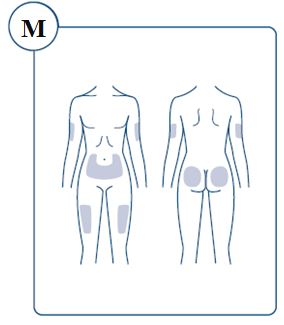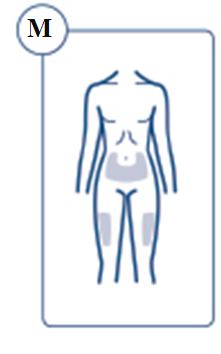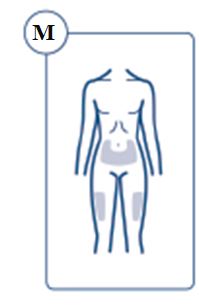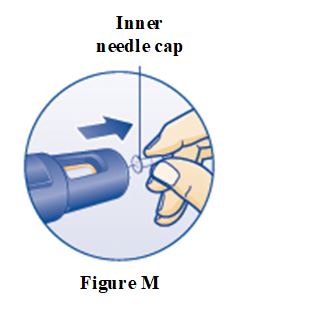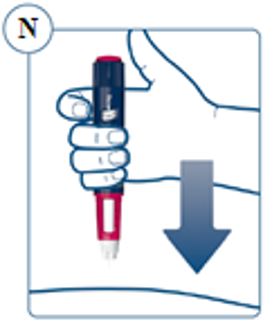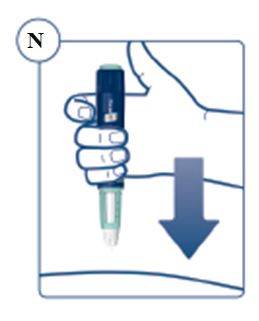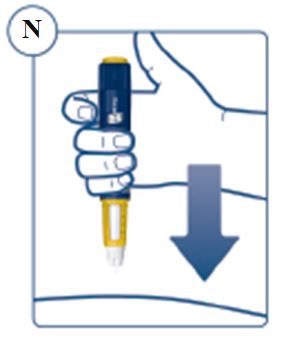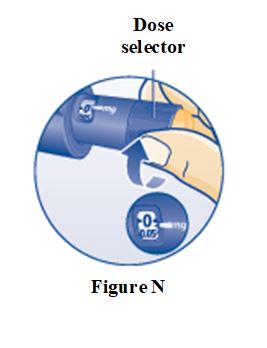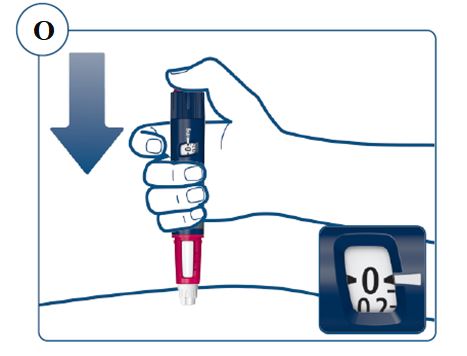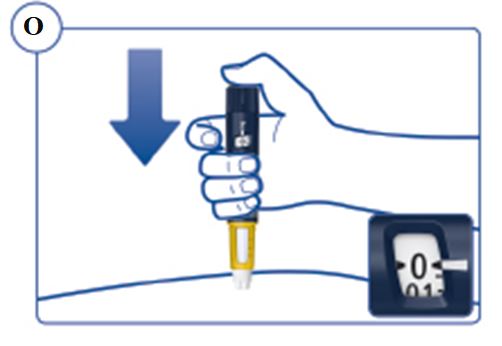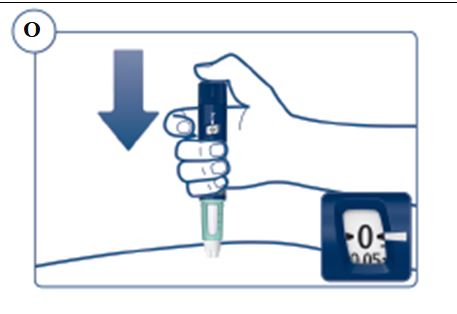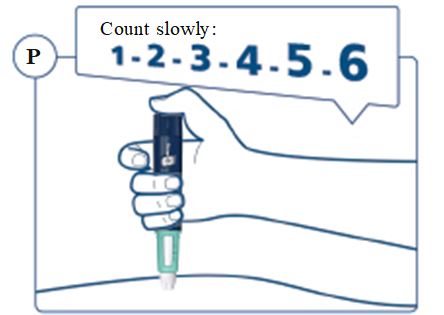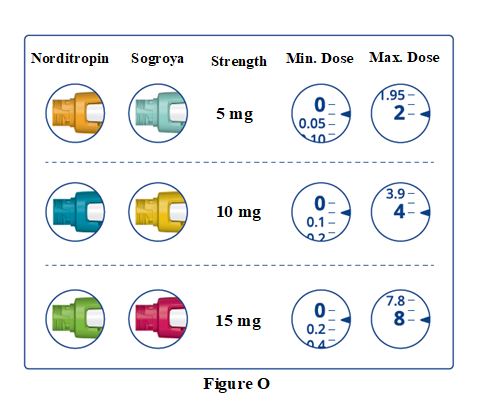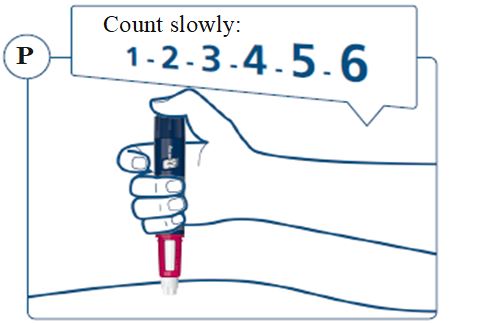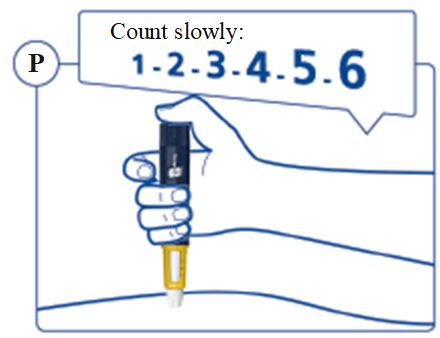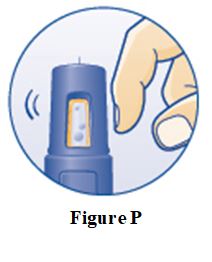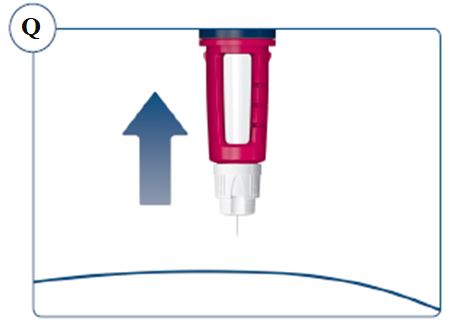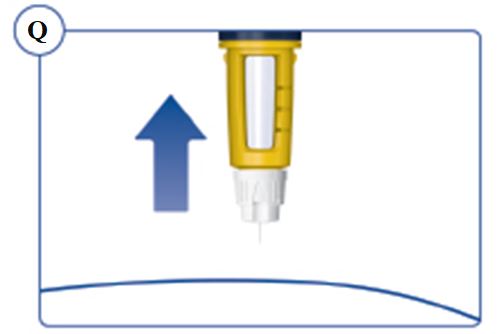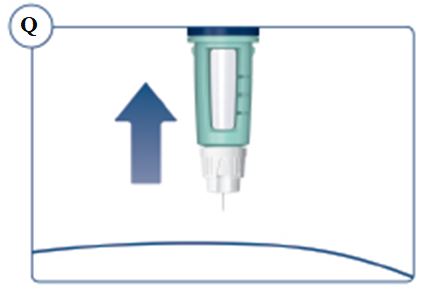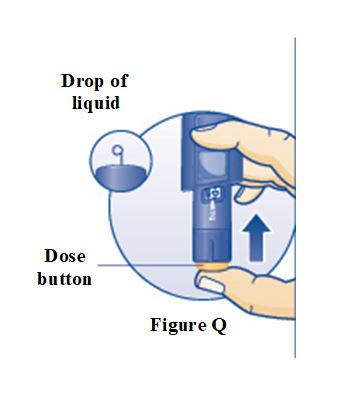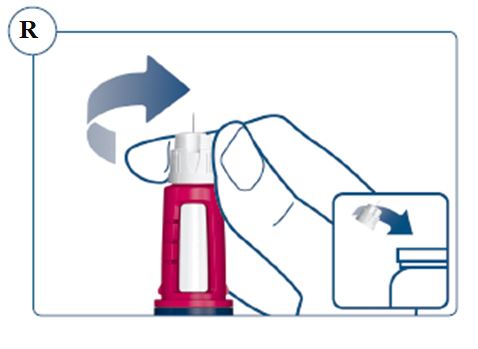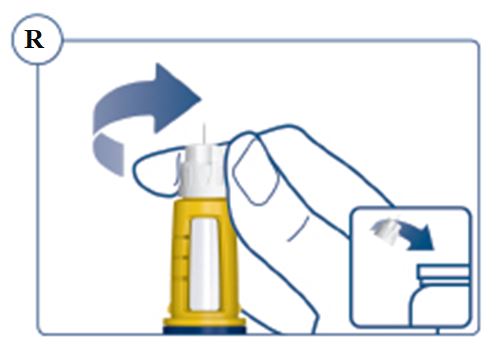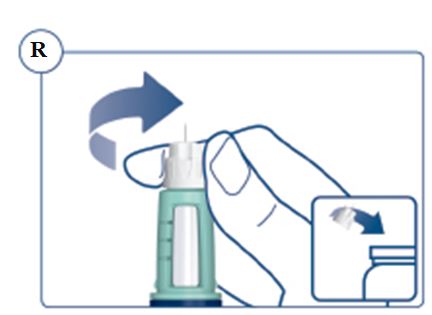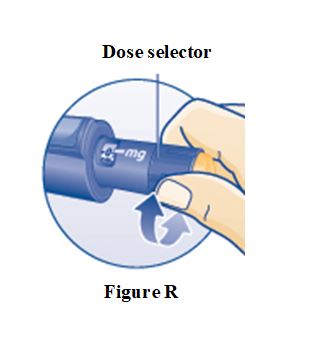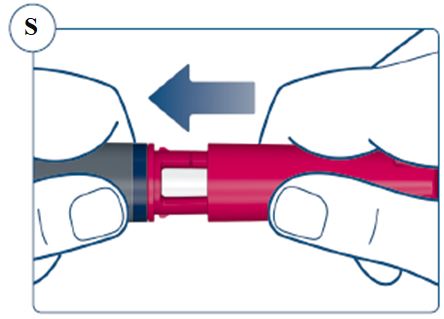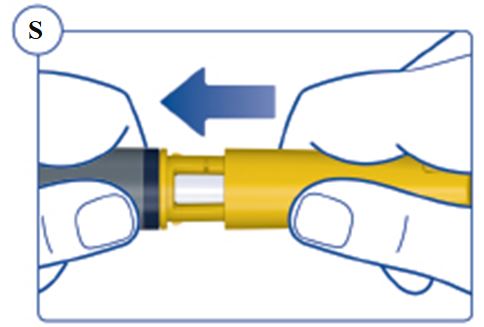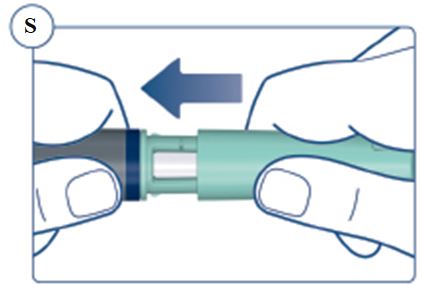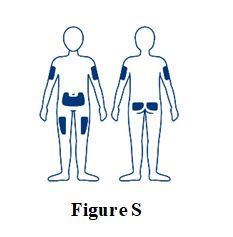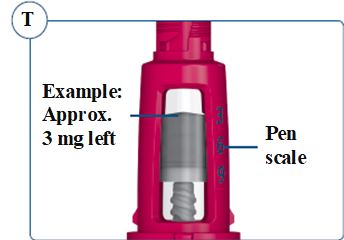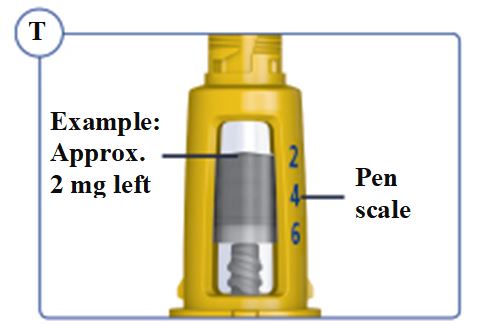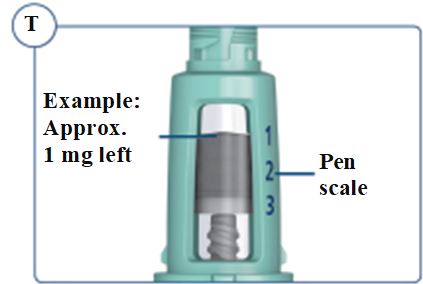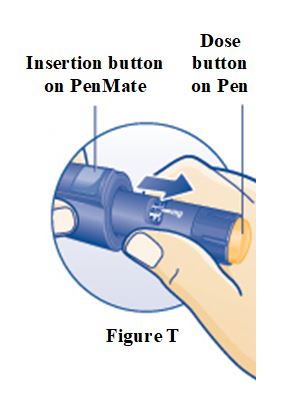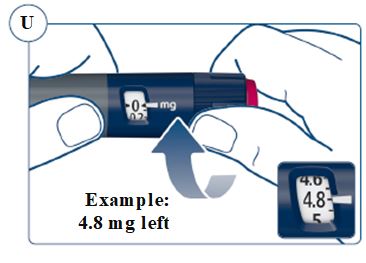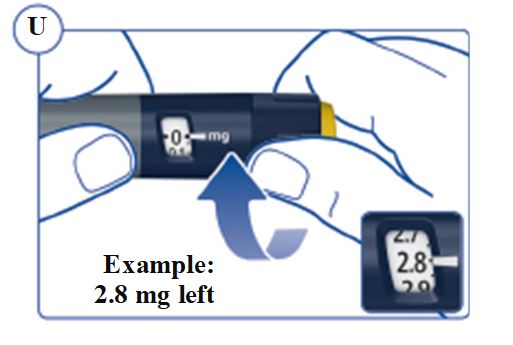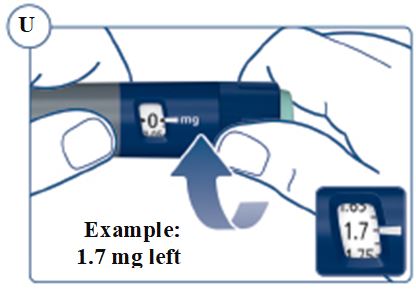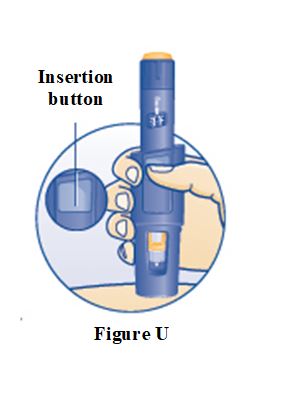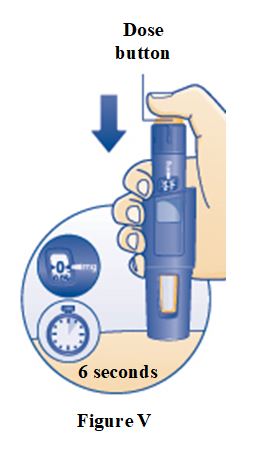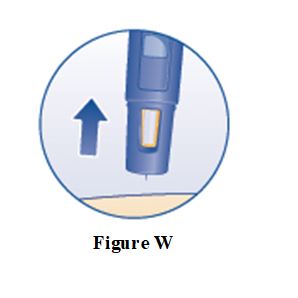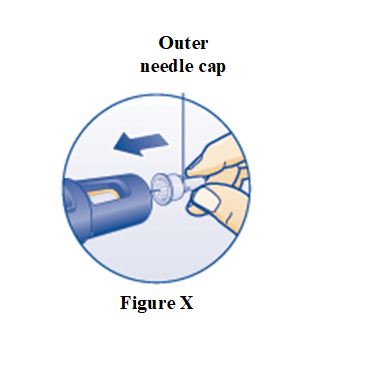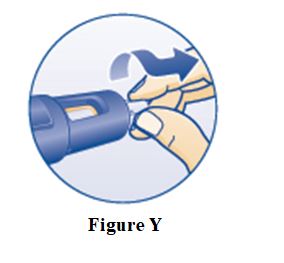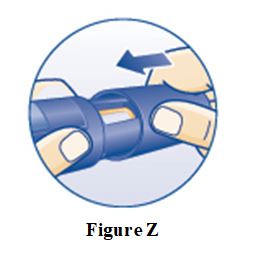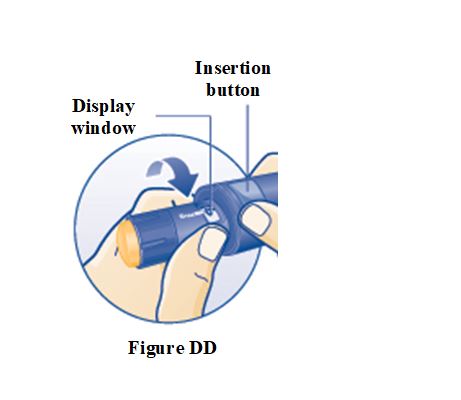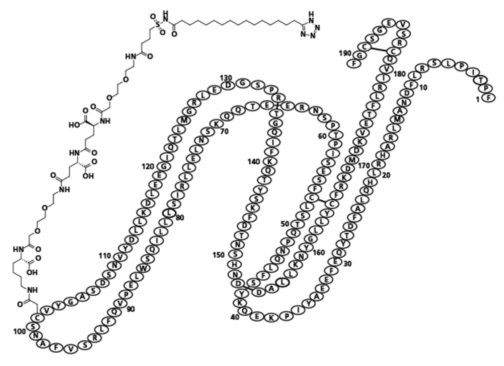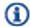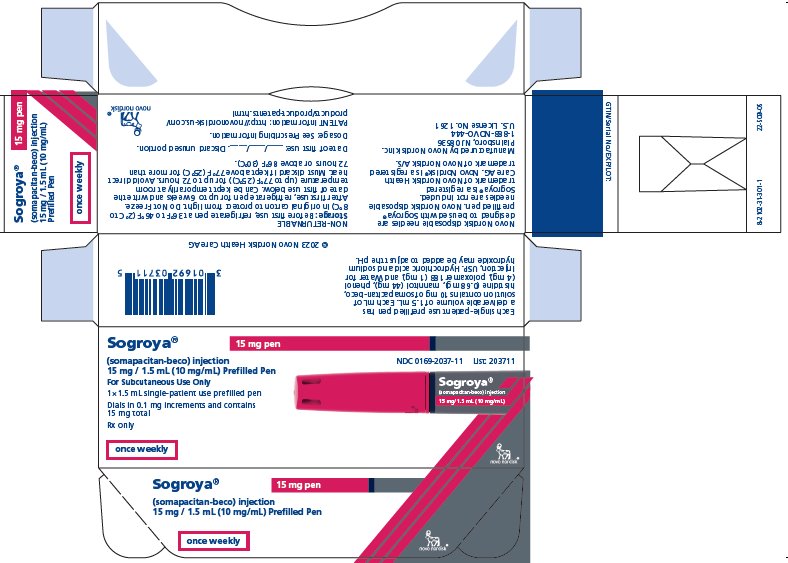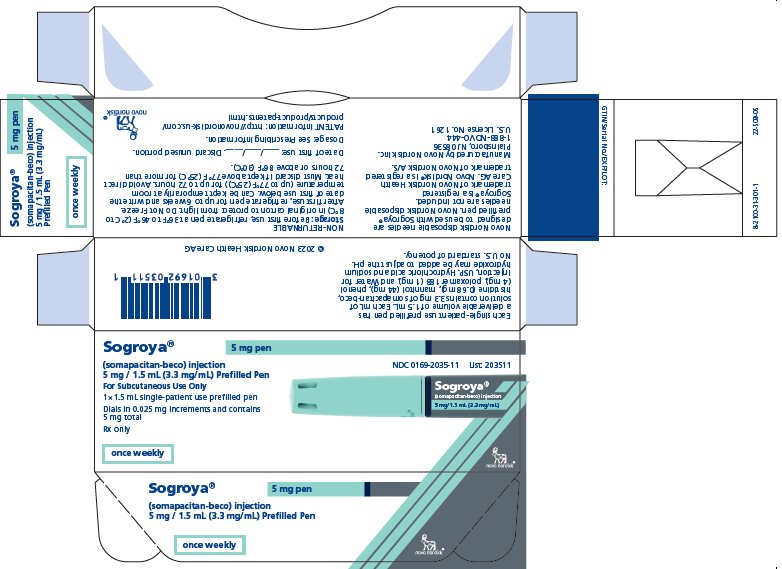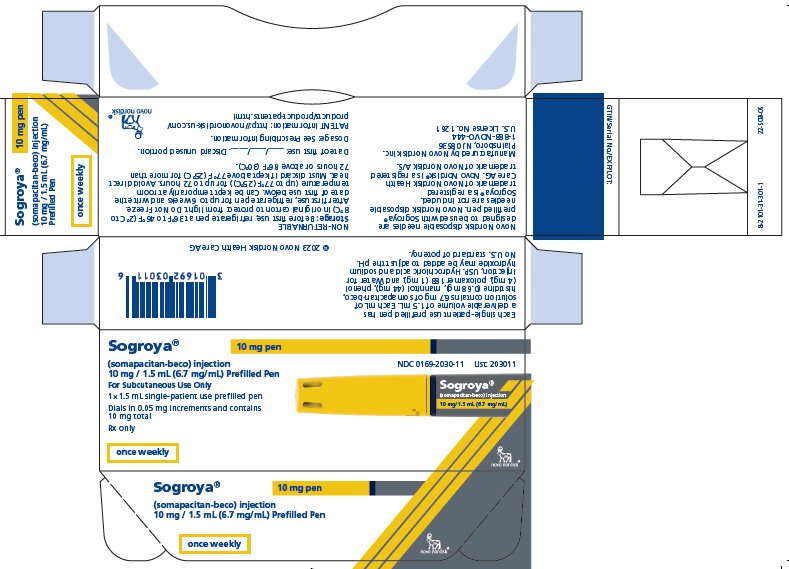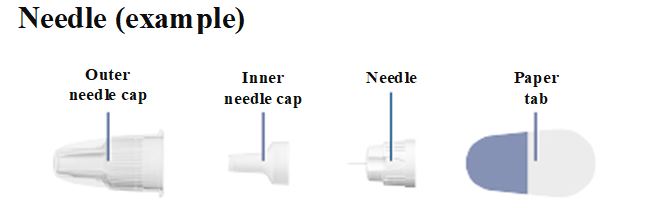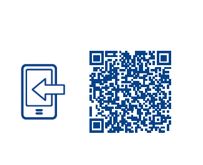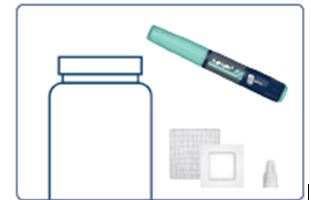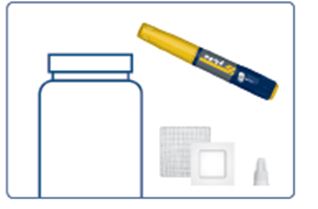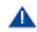 DRUG LABEL: SOGROYA
NDC: 0169-2035 | Form: INJECTION, SOLUTION
Manufacturer: Novo Nordisk
Category: prescription | Type: HUMAN PRESCRIPTION DRUG LABEL
Date: 20250707

ACTIVE INGREDIENTS: SOMAPACITAN 3.3 mg/1 mL
INACTIVE INGREDIENTS: HISTIDINE 0.68 mg/1 mL; MANNITOL 44 mg/1 mL; PHENOL 4 mg/1 mL; POLOXAMER 188 1 mg/1 mL; WATER

HIGHLIGHTS OF PRESCRIBING INFORMATION

These highlights do not include all the information needed to use SOGROYA safely and effectively. See full prescribing information for SOGROYA.
SOGROYA® (somapacitan-beco) injection, for subcutaneous use
Initial U.S. Approval: 2020

RECENT MAJOR CHANGES

Warnings and Precautions, Slipped Capital Femoral Epiphysis in Pediatric Patients (5.9)…..07/2025

1 INDICATIONS AND USAGE

SOGROYA is a human growth hormone analog indicated for:

Pediatric Patients: Treatment of pediatric patients aged 2.5 years and older who have growth failure due to inadequate secretion of endogenous growth hormone (GH) (1).

Adults: Replacement of endogenous growth hormone in adults with growth hormone deficiency (1).

2 DOSAGE AND ADMINISTRATION

- SOGROYA treatment should be supervised by a healthcare provider who is experienced in the diagnosis and management of patients with growth hormone deficiency (2.1).
- SOGROYA should be administered by subcutaneous injection once weekly, any time of the day, in the upper arms, thigh, abdomen or buttocks with regular rotation of injection site to avoid lipohypertrophy/lipoatrophy (2.1).
- See Full Prescribing Information for complete dosage, titration, and monitoring recommendations for pediatric and adult patients, including those aged 65 years and older, patients with hepatic impairment, and women receiving oral estrogen (2.1, 2.2, 2.3, 2.4, 2.5).
For pediatric patients with GHD:
- Initiate SOGROYA with a dosage of 0.16 mg/kg body weight once weekly for treatment-naïve patients and patients switching from daily growth hormone (somatropin) (2.3).
- Individualize dosage for each patient based on the growth response (2.3).
- Patients switching from daily human growth hormone to once-weekly SOGROYA should choose the preferred day for the weekly dose and stop final dose of daily treatment the day before (or at least 8 hours before) taking the first dose of once-weekly somapacitan-beco (2.3).
For adult patients with GHD:
- Initiate SOGROYA with a dosage of 1.5 mg once weekly for treatment naïve patients and patients switching from daily growth hormone (2.4).
- Increase the weekly dosage every 2 to 4 weeks by approximately 0.5 mg to 1.5 mg until the desired response has been achieved (2.4).
- Titrate the dosage based on clinical response and serum insulin-like growth factor-1 (IGF-1) concentrations (2.4).
- The maximum recommended dosage for adult GHD is 8 mg once weekly (2.4).

3 DOSAGE FORMS AND STRENGTHS

SOGROYA is a liquid solution available in a ready-to-use prefilled pen.

Injection: 5 mg/1.5 mL (3.3 mg/mL) or 10 mg/1.5 mL (6.7 mg/mL) or 15 mg/1.5 mL (10 mg/mL) in a single-patient-use prefilled pen (3).

4 CONTRAINDICATIONS

- Acute critical illness (4)
- Active malignancy (4)
- Hypersensitivity to somapacitan-beco or excipients (4)
- Active proliferative or severe non-proliferative diabetic retinopathy (4)
- Closed epiphyses in children used for longitudinal growth promotion (4)
- Children with Prader-Willi syndrome who are severely obese or have severe respiratory impairment due to risk of sudden death (4)

5 WARNINGS AND PRECAUTIONS

- Severe Hypersensitivity: Serious hypersensitivity reactions, including anaphylactic reactions and angioedema, may occur. In the event of an allergic reaction, seek prompt medical attention (5.2).
- Increased Risk of Neoplasm: Monitor patients with preexisting tumors for progression or recurrence. Increased risk of a second neoplasm in childhood cancer survivors treated with somatropin – in particular meningiomas in patients treated with radiation to the head for their first neoplasm (5.3).
- Glucose Intolerance and Diabetes Mellitus: SOGROYA may decrease insulin sensitivity, particularly at higher doses. Monitor glucose levels periodically in all patients receiving SOGROYA, especially in patients with existing diabetes mellitus or at risk for its development (5.4).
- Intracranial Hypertension (IH): Perform fundoscopic examinations prior to initiation and periodically thereafter. If papilledema is identified prior to initiation, evaluate the etiology and treat the underlying cause before initiating. If papilledema occurs with SOGROYA, stop treatment (5.5).
- Fluid Retention: May occur and may be dose dependent. Reduce dose as necessary (5.6).
- Hypoadrenalism: Monitor patients for reduced serum cortisol levels and/or need for glucocorticoid dose increases in those with known hypoadrenalism (5.7).
- Hypothyroidism: Monitor thyroid function periodically as hypothyroidism may occur or worsen after initiation of SOGROYA (5.8).
- Slipped Capital Femoral Epiphysis in Pediatric Patients: May develop. Evaluate children with the onset of a limp or persistent hip/knee pain (5.9).
- Progression of Preexisting Scoliosis in Pediatric Patients: May develop (5.10).
- Pancreatitis: Consider pancreatitis in patients with persistent severe abdominal pain (5.11).
- Lipohypertrophy/lipoatrophy: May occur if SOGROYA is administered in the same location over a long period of time. Rotate injection sites on a regular basis (5.12).

6 ADVERSE REACTIONS

- Pediatric patients with GHD: Adverse reactions reported in ≥5% of patients treated with SOGROYA are: nasopharyngitis, headache, pyrexia, pain in extremity, and injection site reaction (6.1).
- Adult patients with GHD: Adverse reactions reported in >2% of patients treated with SOGROYA are: back pain, arthralgia, dyspepsia, sleep disorder, dizziness, tonsillitis, peripheral edema, vomiting, adrenal insufficiency, hypertension, blood creatine phosphokinase increase, weight increase, anemia (6.1).

To report SUSPECTED ADVERSE REACTIONS, contact Novo Nordisk Inc. at 1-800-727-6500 or FDA at 1-800-FDA-1088 or www.fda.gov/medwatch.

7 DRUG INTERACTIONS

- Replacement Glucocorticoid Treatment: Patients treated with glucocorticoid for hypoadrenalism may require an increase in their maintenance or stress doses following initiation of SOGROYA (7).
- Cytochrome P450-Metabolized Drugs: SOGROYA may alter the clearance. Monitor carefully if used with SOGROYA (7).
- Oral Estrogen: Larger doses of SOGROYA may be required (7).
- Insulin and/or Other Antihyperglycemic Agents: Dose adjustment of insulin or antihyperglycemic agent may be required (5.4, 7).

FULL PRESCRIBING INFORMATION

1 INDICATIONS AND USAGE

SOGROYA is indicated for the:

- Treatment of pediatric patients aged 2.5 years and older who have growth failure due to inadequate secretion of endogenous growth hormone (GH).
- Replacement of endogenous GH in adults with growth hormone deficiency (GHD).

2 DOSAGE AND ADMINISTRATION

2.1 Important Dosing and Administration Information

- SOGROYA treatment should be supervised by a healthcare provider who is experienced in the diagnosis and management of pediatric patients with growth failure due to GHD and/or adults with GHD [see Indications and Usage (1)].
- SOGROYA should be administered by subcutaneous injection, once weekly, any time of the day, in the upper arms, thigh, abdomen or buttocks with weekly rotation of injection site.
- Inspect visually for particulate matter and discoloration. SOGROYA should be a clear to slightly opalescent and colorless to slightly yellow solution. If the solution is cloudy or contains particulate matter do not use.
- Advise patients to read the PATIENT INFORMATION and INSTRUCTIONS FOR USE leaflets enclosed with the SOGROYA prefilled pen.
- SOGROYA is available in 3 single-patient-use prefilled pens with 3 different dosing ranges (Table 1).
Table 1. Strength and Dosing Range of SOGROYA prefilled pens

Strength | Dose increments (mg) | Dose Delivery Range (mg)
5 mg/1.5 mL (3.3 mg/mL) | 0.025 | 0.025 to 2
10 mg/1.5 mL (6.7 mg/mL) | 0.05 | 0.05 to 4
15 mg/1.5 mL (10 mg/mL) | 0.1 | 0.1 to 8

2.2 Perform Fundoscopic Examination Prior to Initiation of SOGROYA

- Perform fundoscopic examination before initiating treatment with SOGROYA to exclude preexisting papilledema. If papilledema is identified, evaluate the etiology and treat the underlying cause before initiating treatment with SOGROYA [see Warnings and Precautions (5.5)].

2.3 Recommended Dosage and Monitoring for Pediatric Patients with GHD

- Recommended dosage of SOGROYA is 0.16 mg/kg based on actual body weight once weekly for treatment-naïve patients and patients switching from daily growth hormone (somatropin).
- Individualize dosage for each patient based on the growth response.
- When switching from daily human growth hormone to once-weekly SOGROYA, choose the preferred day for the weekly dose. Take the final dose of daily treatment on the day before (or at least 8 hours before) the first dose of SOGROYA.
- When switching from a weekly human growth hormone to once-weekly SOGROYA, continue once weekly dosing schedule.
- Assess compliance and evaluate other causes of poor growth such as hypothyroidism, undernutrition, advanced bone age, and antibodies to recombinant human growth hormone if patients experience failure to increase height velocity, particularly during the first year of treatment.
- Patients who were treated with SOGROYA for GH deficiency in childhood and whose epiphyses are closed should be reevaluated before continuing SOGROYA.

2.4 Recommended Dosage, Titration, and Monitoring for Adult Patients with GHD

- Initiate SOGROYA with a dosage of 1.5 mg once weekly for treatment naïve patients and patients switching from daily growth hormone (somatropin).
- Increase the weekly dosage every 2 to 4 weeks by approximately 0.5 mg to 1.5 mg until the desired response is achieved.
- Titrate the dosage based on clinical response and serum insulin-like growth factor-1 (IGF-1) concentrations. Draw IGF-1 samples 3 to 4 days after the prior dose.
- Decrease the dosage as necessary on the basis of adverse reactions and/or serum IGF-1 concentrations above the age- and sex-specific normal range.
- The maximum recommended dosage is 8 mg once weekly.

2.5 Recommended Dosage and Titration for Specific Populations

Patients Aged 65 Years and Older

Initiate SOGROYA with a dosage of 1 mg once weekly and use smaller dose increment increases when titrating the dosage [see Use in Specific Populations (8.5)]. See above for monitoring recommendations and the maximum recommended dosage of SOGROYA [see Dosage and Administration (2.4)].

Patients with Hepatic Impairment

- SOGROYA is not recommended in adult and pediatric patients with severe hepatic impairment [see Hepatic Impairment (8.6)].
- For adult patients with moderate hepatic impairment, initiate SOGROYA with a dosage of 1 mg once weekly and use smaller dose increment increases when titrating the dosage. See above for monitoring recommendations [see Dosage and Administration (2.4) and Pharmacokinetics (12.3)]. The maximum recommended dosage is 4 mg once weekly.
- For pediatric patients with moderate hepatic impairment, SOGROYA is not recommended [see Hepatic Impairment (8.6)].
- No dosage adjustment is recommended for adult and pediatric patients with mild hepatic impairment.

Women Receiving Oral Estrogen

Initiate SOGROYA with a dosage of 2 mg once weekly [see Drug Interactions (7)]. See above for titration and monitoring recommendations and the maximum recommended dosage of SOGROYA [see Dosage and Administration (2.4)].

2.6 Missed Doses

- If the dose is missed, SOGROYA can be taken within 3 days after the scheduled dosing day. Once-weekly dosing for the next dose could be resumed at the regularly scheduled dosing day.
- If more than 3 days have passed since the missed dose, skip the dose and administer the next dose on the regularly scheduled dosing day.

3 DOSAGE FORMS AND STRENGTHS

SOGROYA is a clear to slightly opalescent and colorless to slightly yellow solution available as follows:

- Injection: 5 mg/1.5 mL (3.3 mg/mL) in a single-patient-use prefilled pen (teal)
- Injection: 10 mg/1.5 mL (6.7 mg/mL) in a single-patient-use prefilled pen (yellow)
- Injection: 15 mg/1.5 mL (10 mg/mL) in a single-patient-use prefilled pen (red)

4 CONTRAINDICATIONS

SOGROYA is contraindicated in patients with:

- Acute critical illness after open-heart surgery, abdominal surgery or multiple accidental trauma, or those with acute respiratory failure because of the risk of increased mortality with use of pharmacologic doses of SOGROYA [see Warnings and Precautions (5.1)].
- Hypersensitivity to SOGROYA or any of its excipients. Systemic hypersensitivity reactions have been reported postmarketing with somatropin [see Warnings and Precautions (5.2)].
- Pediatric patients with closed epiphyses.
- Active malignancy [see Warnings and Precautions (5.3)].
- Active proliferative or severe non-proliferative diabetic retinopathy.
- Pediatric patients with Prader-Willi syndrome who are severely obese, have a history of upper airway obstruction or sleep apnea or have severe respiratory impairment due to risk of sudden death [see Warnings and Precautions (5.13)].

5 WARNINGS AND PRECAUTIONS

5.1 Increased Mortality in Patients with Acute Critical Illness

Increased mortality has been reported after treatment with somatropin in patients with acute critical illness due to complications following open-heart surgery, abdominal surgery and multiple accidental trauma, as well as patients with acute respiratory failure [see Contraindications (4)]. The safety of continuing SOGROYA treatment in patients receiving replacement doses for approved indications who concurrently develop these illnesses has not been established. SOGROYA is not indicated for the treatment of non-GH deficient adults.

5.2 Severe Hypersensitivity

Serious systemic hypersensitivity reactions including anaphylactic reactions and angioedema have been reported with postmarketing use of somatropin. Inform patients and/or caregivers that such reactions are possible, and that prompt medical attention should be sought if an allergic reaction occurs. SOGROYA is contraindicated in patients with known hypersensitivity to somatropin or any excipients in SOGROYA [see Contraindications (4)].

5.3 Increased Risk of Neoplasms

Active Malignancy

There is an increased risk of malignancy progression with somatropin treatment in patients with active malignancy [see Contraindications (4)]. Any preexisting malignancy should be inactive, and its treatment complete prior to instituting therapy with SOGROYA. Discontinue SOGROYA if there is evidence of recurrent activity.

Risk of Second Neoplasm in Pediatric Patients

In childhood cancer survivors who were treated with radiation to the brain/head for their first neoplasm and who developed subsequent growth hormone deficiency (GHD) and were treated with somatropin, an increased risk of second neoplasm has been reported. Intracranial tumors, in particular meningiomas, were the most common of these second neoplasms. Monitor all patients with a history of GHD secondary to an intracranial neoplasm while on somatropin therapy for progression or recurrence of the tumor.

New Malignancy During Treatment

Because children with certain rare genetic causes of short stature have an increased risk of developing malignancies, thoroughly consider the risks and benefits of starting SOGROYA in these patients. If treatment with SOGROYA is initiated, carefully monitor these patients for development of neoplasms.

There is risk of malignant changes of preexisting nevi with somatropin treatment in patients. Monitor patients on SOGROYA therapy carefully for increased growth or potential malignant changes of preexisting nevi. Advise patients/caregivers to report marked changes in behavior, onset of headaches, vision disturbances, and/or changes in the appearance of preexisting nevi.

5.4 Glucose Intolerance and Diabetes Mellitus

Treatment with somatropin may decrease insulin sensitivity, particularly at higher doses. New onset type 2 diabetes mellitus has been reported in patients taking somatropin. Patients with undiagnosed pre-diabetes and diabetes mellitus may experience worsened glycemic control and become symptomatic. Monitor glucose levels periodically in all patients receiving SOGROYA, especially in those with risk factors for diabetes mellitus, such as obesity, Turner syndrome, or a family history of diabetes mellitus. Patients with preexisting type 1 or type 2 diabetes mellitus or pre-diabetes should be monitored closely. The doses of antidiabetic agents may require adjustment when SOGROYA is initiated.

5.5 Intracranial Hypertension

Intracranial hypertension with papilledema, visual changes, headache, nausea, and/or vomiting has been reported in patients treated with somatropin. Symptoms usually occurred within the first eight (8) weeks after the initiation of somatropin therapy. In all reported cases, intracranial hypertension-associated signs and symptoms rapidly resolved after cessation of therapy or a reduction of the somatropin dose.

Perform fundoscopic examination before initiating treatment with SOGROYA to exclude preexisting papilledema and periodically thereafter. If papilledema is identified prior to initiation, evaluate the etiology and treat the underlying cause before initiating SOGROYA. If papilledema is observed by fundoscopy during SOGROYA treatment, treatment should be stopped. If intracranial hypertension is confirmed, treatment with SOGROYA can be restarted at a lower dose after intracranial hypertension-associated signs and symptoms have resolved.

5.6 Fluid Retention

Fluid retention during SOGROYA replacement therapy may occur. Clinical manifestations of fluid retention (e.g. edema and nerve compression syndromes including carpal tunnel syndrome/paresthesia) are usually transient and dose dependent.

5.7 Hypoadrenalism

Patients receiving somatropin therapy who have or are at risk for corticotropin deficiency may be at risk for reduced serum cortisol levels and/or unmasking of central (secondary) hypoadrenalism. In addition, patients treated with glucocorticoid replacement for previously diagnosed hypoadrenalism may require an increase in their maintenance or stress doses following initiation of SOGROYA treatment. Monitor patients with known hypoadrenalism for reduced serum cortisol levels and/or need for glucocorticoid dose increases [see Drug Interactions (7)].

5.8 Hypothyroidism

Undiagnosed/untreated hypothyroidism may prevent an optimal response to SOGROYA. In patients with GH deficiency, central (secondary) hypothyroidism may first become evident or worsen during treatment with somatropin therapy. Therefore, patients should have periodic thyroid function tests and thyroid hormone replacement therapy should be initiated or appropriately adjusted when indicated.

5.9 Slipped Capital Femoral Epiphysis in Pediatric Patients

Slipped capital femoral epiphysis may occur more frequently in patients undergoing rapid growth. Slipped capital femoral epiphysis may lead to osteonecrosis. Cases of slipped capital femoral epiphysis with or without osteonecrosis have been reported in pediatric patients with short stature receiving somatropin. Evaluate pediatric patients receiving SOGROYA with the onset of a limp or complaints of persistent hip or knee pain for slipped capital femoral epiphysis and osteonecrosis and manage accordingly.

5.10 Progression of Preexisting Scoliosis in Pediatric Patients

Somatropin increases growth rate, and progression of preexisting scoliosis can occur in patients who experience rapid growth. Somatropin has not been shown to increase the occurrence of scoliosis. Monitor patients with a history of scoliosis for disease progression.

5.11 Pancreatitis

Cases of pancreatitis have been reported in patients receiving somatropin. The risk may be greater in pediatric patients compared with adults. Consider pancreatitis in patients who develop persistent severe abdominal pain.

5.12 Lipohypertrophy/Lipoatrophy

When SOGROYA is administered subcutaneously at the same site over a long period of time, tissue lipohypertrophy or lipoatrophy may result. Rotate injection sites when administering SOGROYA to reduce this risk [see Dosage and Administration (2.1)].

5.13 Sudden Death in Pediatric Patients with Prader-Willi Syndrome

There have been reports of fatalities after initiating therapy with somatropin in pediatric patients with Prader-Willi syndrome who had one or more of the following risk factors: severe obesity, history of upper airway obstruction or sleep apnea, or unidentified respiratory infection. Male patients with one or more of these factors may be at greater risk than females. SOGROYA is not indicated for the treatment of pediatric patients who have growth failure due to genetically confirmed Prader-Willi syndrome.

5.14 Laboratory Tests

Serum levels of inorganic phosphorus and alkaline phosphatase may increase after SOGROYA therapy. Serum levels of parathyroid hormone may increase with somatropin treatment.

6 ADVERSE REACTIONS

The following clinically significant adverse drug reactions are described elsewhere in the labeling:

- Increased mortality in patients with acute critical illness [see Warnings and Precautions (5.1)]
- Severe hypersensitivity [see Warnings and Precautions (5.2)]
- Increased risk of neoplasms [see Warnings and Precautions (5.3)]
- Glucose intolerance and diabetes mellitus [see Warnings and Precautions (5.4)]
- Intracranial hypertension [see Warnings and Precautions (5.5)]
- Fluid retention [see Warnings and Precautions (5.6)]
- Hypoadrenalism [see Warnings and Precautions (5.7)]
- Hypothyroidism [see Warnings and Precautions (5.8)]
- Slipped capital femoral epiphysis in pediatric patients [see Warnings and Precautions (5.9)]
- Progression of preexisting scoliosis in pediatric patients [see Warnings and Precautions (5.10)]
- Pancreatitis [see Warnings and Precautions (5.11)]
- Lipohypertrophy/Lipoatrophy [see Warnings and Precautions (5.12)]
- Sudden death in pediatric patients with Prader-Willi syndrome [see Warnings and Precautions (5.13)]

6.1 Clinical Trials Experience

Because clinical trials are conducted under widely varying conditions, adverse reaction rates observed in the clinical trials of a drug cannot be directly compared to rates in the clinical trials of another drug and may not reflect the rates observed in practice.

Pediatric Patients with GHD

SOGROYA was studied in a 52-week randomized, open-label, active-controlled, parallel-group clinical study in 200 treatment-naïve, prepubertal pediatric patients with growth hormone deficiency [see Clinical Studies (14.1)]. Table 2 shows common adverse reactions that occurred in ≥5% of patients treated with either SOGROYA or somatropin in this trial.

Table 2. Adverse Reactions occurring ≥5% in SOGROYA or Somatropin-Treated Pediatric Patients (52 Weeks of Treatment)

 | Somatropin; (N=68) | SOGROYA; (N=132)
Adverse Reactions | % | %
Nasopharyngitis a | 16.2 | 16.7
Headache | 8.8 | 12.1
Pyrexiab | 11.8 | 9.1
Pain in extremityc | 2.9 | 9.8
Injection site reactiond | 5.9 | 6.1
Diarrheae | 5.9 | 4.5
Nausea/vomitingf | 5.9 | 4.5
Bronchitis | 7.4 | 3

aNasopharyngitis in the SOGROYA treatment group included nasopharyngitis (11.4%), rhinitis (3.8%), pharyngitis streptococcal (0.8%), acute sinusitis (0.8%), nasal congestion (0.8%), pharyngitis (0.8%), and sinusitis (0.8%).
bPyrexia in the SOGROYA treatment group included pyrexia (8.3%) and hyperthermia (0.8%).
cPain in extremity in the SOGROYA treatment group included pain in extremity (9.1%) and growing pains (0.8%).
dInjection site reaction in the SOGROYA treatment group included injection site bruising (1.5%), injection site pain (1.5%), injection site hematoma (1.5%), injection site reaction (0.8%), and injection site swelling (0.8%)
eDiarrhea in the SOGROYA treatment group included diarrhea (2.3%), gastroenteritis viral (1.5%), and gastrointestinal viral infection (0.8%)
fNausea/vomiting in the SOGROYA treatment group included vomiting (4.5%) and nausea (1.5%)

Adult Patients with GHD

SOGROYA was studied in adult patients with GHD in a 35-week, placebo-controlled, double-blind trial with an active-control arm [see Clinical Studies (14.2)]. Adverse reactions occurring >2% with SOGROYA are presented in Table 3.

Table 3. Adverse Reactions occurring >2% in Adults with GHD Treated with SOGROYA and More Frequently# than in Placebo-Treated Patients for 34 Weeks

 | Placebo; (N=61) | SOGROYA; (N=120)
Adverse Reactions | % | %
Back pain | 3.3 | 10
Arthralgia | 1.6 | 6.7
Dyspepsia | 3.3 | 5
Sleep disorder | 1.6 | 4.2
Dizziness | 1.6 | 4.2
Tonsillitis | 1.6 | 3.3
Peripheral edema | 1.6 | 3.3
Vomiting | 1.6 | 3.3
Adrenal insufficiency | 1.6 | 3.3
Hypertension | 1.6 | 3.3
Blood creatine phosphokinase increase | 0 | 3.3
Weight increased | 0 | 3.3
Anemia | 0 | 2.5

# Included adverse reactions reported with at least 1% greater incidence in SOGROYA group compared to the placebo group

More SOGROYA treated patients shifted from normal baseline levels to elevated phosphate and creatine phosphokinase levels at the end of the trial compared to the placebo group (17.5% vs 4.9% and 9.2% vs. 6.6%, respectively); these laboratory changes occurred intermittently, and were non-progressive.

6.2 Postmarketing Experience

The following adverse reactions have been identified during post-approval use of somatropins. Because these reactions are reported voluntarily from a population of uncertain size, it is not always possible to reliably estimate their frequency or establish a causal relationship to drug exposure.

Musculoskeletal and connective tissue disorders – osteonecrosis in pediatric patients.

7 DRUG INTERACTIONS

Table 4 includes a list of drugs with clinically important drug interactions when administered concomitantly with SOGROYA and instructions for preventing or managing them.

Table 4. Clinically Important Drug Interactions with SOGROYA

Replacement Glucocorticoid Treatment
Clinical Impact: | Microsomal enzyme 11β-hydroxysteroid dehydrogenase type 1 (11βHSD-1) is required for conversion of cortisone to its active metabolite, cortisol, in hepatic and adipose tissue. GH inhibits 11βHSD-1. Consequently, individuals with untreated GH deficiency have relative increases in 11βHSD-1 and serum cortisol. Initiation of SOGROYA may result in inhibition of 11βHSD-1 and reduced serum cortisol concentrations.
Intervention: | Patients treated with glucocorticoid replacement for hypoadrenalism may require an increase in their maintenance or stress doses following initiation of SOGROYA [see Warnings and Precautions (5.7)].
Examples: | Cortisone acetate and prednisone may be affected more than others because conversion of these drugs to their biologically active metabolites is dependent on the activity of 11βHSD-1.
Cytochrome P450-Metabolized Drugs
Clinical Impact: | Limited published data indicate that GH treatment increases cytochrome P450 (CP450)-mediated antipyrine clearance. SOGROYA may alter the clearance of compounds known to be metabolized by CP450 liver enzymes.
Intervention: | Careful monitoring is advisable when SOGROYA is administered in combination with drugs metabolized by CP450 liver enzymes.
Oral Estrogen
Clinical Impact: | Oral estrogens may reduce the serum IGF-1 response to SOGROYA.
Intervention: | Patients receiving oral estrogen replacement may require higher SOGROYA dosages [see Dosage and Administration (2.5)].
Insulin and/or Other Hypoglycemic Agents
Clinical Impact: | Treatment with SOGROYA may decrease insulin sensitivity, particularly at higher doses.
Intervention: | Patients with diabetes mellitus may require adjustment of their doses of insulin and/or other hypoglycemic agents [see Warnings and Precautions (5.4)].

8 USE IN SPECIFIC POPULATIONS

8.1 Pregnancy

Risk Summary

There are no available data on the use of SOGROYA during pregnancy; however, published studies describing the use of short-acting recombinant growth hormone (rhGH) during pregnancy over several decades have not identified any drug-associated risk of major birth defects, miscarriage, or adverse maternal or fetal outcomes. In animal reproduction studies, subcutaneously administered somapacitan-beco was not teratogenic in rats or rabbits during organogenesis at doses approximately 12 times the clinical exposure at the maximum recommended human dose (MRHD) of 8 mg/week. No adverse developmental outcomes were observed in a pre- and post-natal development study with administration of somapacitan-beco to pregnant rats from organogenesis through lactation at approximately 275 times the clinical exposure at the MRHD (see Data).

The background risk of birth defects and miscarriage for the indicated population is unknown. In the U.S. general population, the estimated background risk of major birth defects and miscarriage in clinically recognized pregnancies is 2 to 4% and 15 to 20%, respectively.

Data

Animal Data

In an embryo-fetal development study in rats, somapacitan-beco was administered by subcutaneous injection at doses of 2, 6, and 18 mg/kg/day during the period of organogenesis from gestation day 6 to 17. Fetal viability and development were not affected at doses up to 6 mg/kg/day (31 times the MRHD, based on AUC). Transient, fetal skeletal variations (short/bent/thickened long bones) were observed at 18 mg/kg/day (261 times the MRHD, based on AUC).

In an embryo-fetal development study in rabbits, somapacitan-beco was administered by subcutaneous injection at doses of 1, 3, and 9 mg/kg every two days during the period of organogenesis from gestation day 6 to 18. Fetal viability and development were not adversely affected at somapacitan-beco dose of 1 mg/kg/every two days (12 times the MRHD, based on AUC). Reduced fetal growth was observed at doses ≥3 mg/kg/every two days (≥130 times the MRHD, based on C12h).

In a pre- and post-natal development study in pregnant rats, somapacitan-beco was administered by subcutaneous injection at doses of 4, 9, and 18 mg/kg twice a week from gestation day 6 through lactation day 18. No adverse developmental effects were observed in the offspring at doses up to 9 mg/kg (275 times the MRHD, based on AUC). Increased incidence of renal pelvic dilatation was observed on post-natal day 21 at 18 mg/kg (630 times the MRHD, based on AUC), but was not observed in the adult F1 generation.

8.2 Lactation

Risk Summary

There is no information on the presence of somapacitan-beco in human milk, the effects on the breastfed infant, or the effects on milk production. Somapacitan-beco-related material was secreted into milk of lactating rats. When a substance is present in animal milk, it is likely that the substance will be present in human milk. Available published data describing administration of short-acting recombinant growth hormone (rhGH) to lactating women for 7 days reported that short-acting rhGH did not increase the normal breastmilk concentration of growth hormone and no adverse effects were reported in breastfed infants. The developmental and health benefits of breastfeeding should be considered along with the mother’s clinical need for SOGROYA and any potential adverse effects on the breastfed infant from SOGROYA or from the underlying maternal condition.

8.4 Pediatric Use

The safety and effectiveness of SOGROYA have been established for the treatment of growth failure due to inadequate secretion of endogenous growth hormone (GH) in pediatric patients 2.5 years of age and older. The use of SOGROYA for this indication is supported by evidence from a 52 week randomized, multi-center, open-label, active-controlled, parallel-group phase 3 trial in 200 treatment-naïve, pediatric patients with GHD. The safety profile from the pediatric trial was similar to that reported in adults [see Adverse Reactions (6.1) and Clinical Studies (14.1)].

Risks in pediatric patients associated with growth hormone use include:

- Sudden death in pediatric patients with Prader-Willi Syndrome. SOGROYA is not indicated for the treatment of pediatric patients with growth failure secondary to genetically confirmed Prader-Willi syndrome.[see Warnings and Precautions (5.13)]
- Increased risk of second neoplasm in pediatric cancer survivors treated with radiation to the brain and/or head [see Warnings and Precautions (5.3)]
- Slipped capital femoral epiphysis in pediatric patients [see Warnings and Precautions (5.9)]
- Progression of preexisting scoliosis in pediatric patients [see Warnings and Precautions (5.10)]
- Pancreatitis [see Warnings and Precautions (5.11)]

The safety and effectiveness of SOGROYA for the treatment of growth failure due to inadequate secretion of endogenous growth hormone have not been established in pediatric patients less than 2.5 years of age.

8.5 Geriatric Use

In clinical studies a total of 52 (15.6%) of the 333 SOGROYA-treated patients were 65 years or older and 3 (0.9%) were 75 years or older [see Clinical Studies (14)]. Subjects older than 65 years appeared to have higher exposure than younger subjects at the same dose level. Elderly patients may be more sensitive to the action of somapacitan-beco, and therefore may be at increased risk for adverse reactions. Initiate SOGROYA with a dose of 1 mg once weekly and use smaller increments when increasing the dose [see Dosage and Administration (2.5)].

8.6 Hepatic Impairment

Adult patients: No dose adjustment of SOGROYA is required for patients with mild hepatic impairment. Higher somapacitan-beco exposure was observed in patients with moderate hepatic impairment. In patients with moderate hepatic impairment, initiate SOGROYA with a dose of 1 mg once weekly and use smaller increments when increasing the dose. The maximum dose should not exceed 4 mg once weekly. Somapacitan-beco was not studied in patients with severe hepatic impairment. Therefore, use of SOGROYA is not recommended in patients with severe hepatic impairment. [see Dosage and Administration (2.5) and Clinical Pharmacology (12.3)].

Pediatric patients: Based on the hepatic impairment study in adults, no dose adjustment of SOGROYA is recommended for patients with mild hepatic impairment. Higher systemic exposure of SOGROYA is expected in pediatric patients with moderate and severe hepatic impairment; therefore, SOGROYA is not recommended in these pediatric patients [see Dosage and Administration (2.5)].

9 DRUG ABUSE AND DEPENDENCE

9.1 Controlled Substance

SOGROYA contains somapacitan-beco, which is not a controlled substance.

9.2 Abuse

Inappropriate use of SOGROYA may result in significant negative health consequences.

9.3 Dependence

SOGROYA is not associated with drug related withdrawal adverse reactions.

10 OVERDOSAGE

Acute overdosage could lead initially to hypoglycemia and subsequently to hyperglycemia. Overdose with SOGROYA is likely to cause fluid retention. Long-term overdosage could result in signs and symptoms of gigantism and/or acromegaly consistent with the known effects of excess endogenous growth hormone.

11 DESCRIPTION

Somapacitan-beco is a human growth hormone (hGH) analog with a single substitution in the amino acid backbone (L101C) to which an albumin-binding moiety has been attached. The albumin-binding moiety (side-chain) consists of an albumin binder and a hydrophilic spacer attached to position 101 of the protein. The protein part consists of 191 amino acids. Somapacitan-beco is produced in Escherichia coli by recombinant DNA technology. The molecular formula (including the albumin-binding moiety) is C1038H1609N273O319S9 and the molecular weight is 23305.10 g/mol, of which the albumin-binding moiety is 1191.39 g/mol.

Structural Formula:

SOGROYA (somapacitan-beco) injection is supplied as a sterile, clear to slightly opalescent and colorless to slightly yellow solution for subcutaneous use in a single-patient-use prefilled pen with a deliverable volume of 1.5 mL.

Each mL of SOGROYA 5 mg/1.5 mL prefilled pen contains 3.3 mg of somapacitan-beco, histidine (0.68 mg), mannitol (44 mg), phenol (4 mg), poloxamer 188 (1 mg), and Water for Injection, USP. The pH is approximately 6.8. Hydrochloric acid and sodium hydroxide may be added to adjust the pH.

Each mL of SOGROYA 10 mg/1.5 mL prefilled pen contains 6.7 mg of somapacitan-beco, histidine (0.68 mg), mannitol (44 mg), phenol (4 mg), poloxamer 188 (1 mg), and Water for Injection, USP. The pH is approximately 6.8. Hydrochloric acid and sodium hydroxide may be added to adjust the pH.

Each mL of SOGROYA 15 mg/1.5 mL prefilled pen contains 10 mg of somapacitan-beco, histidine (0.68 mg), mannitol (44 mg), phenol (4 mg), poloxamer 188 (1 mg), and Water for Injection, USP. The pH is approximately 6.8. Hydrochloric acid and sodium hydroxide may be added to adjust the pH.

12 CLINICAL PHARMACOLOGY

12.1 Mechanism of Action

Somapacitan-beco binds to a dimeric GH receptor in the cell membrane of target cells resulting in intracellular signal transduction and a host of pharmacodynamic effects. Some of these pharmacodynamic effects are primarily mediated by insulin-like growth factor-1 (IGF-1) produced in the liver, while others are primarily a consequence of the direct effects of somapacitan-beco.

12.2 Pharmacodynamics

IGF-1 was measured to assess the pharmacodynamic (PD) properties of somapacitan-beco. Somapacitan-beco normalizes the mean IGF-1 standard deviation score (SDS) level from a baseline value below -2 to a value within the reference range (-2 to +2) in treatment-naïve adult patients with GHD [see Clinical Studies (14)].

In adult patients with GHD (n=26), somapacitan-beco induces a less than dose proportional IGF-1 response at steady state. Maximum IGF-1 concentrations were observed within 2 to 4 days after dosing. Similar to the somapacitan-beco exposure time course, a steady state IGF-1 response was reached after 1 to 2 weekly doses with limited cumulative IGF-1 response.

In pediatric patients with GHD aged 2.5 to 11 years, somapacitan-beco produces a dose linear IGF-1 response, with a change of 0.02 mg/kg on average resulting in a change in IGF-1 standard deviation score (SDS) of 0.32. Approximately 97% of pediatric patients achieved an average IGF-1 SDS level within normal range after 52 weeks of treatment with once weekly Sogroya in Study NCT03811535. IGF-1 SDS levels were -2.03 at baseline and the IGF-1 SDS level change from baseline was 2.36.

12.3 Pharmacokinetics

Somapacitan-beco has pharmacokinetic properties compatible with once weekly administration. The reversible binding to endogenous albumin delays elimination of somapacitan and thereby prolongs the in vivo half-life and duration of action.

The pharmacokinetics (PK) of somapacitan-beco following subcutaneous administration have been investigated at clinically relevant doses (e.g., 0.01 to 0.32 mg/kg in healthy adults, 0.02 to 0.12 mg/kg in adults with GHD, and 0.02 to 0.16 mg/kg in pediatric patient with GHD)‎.

Overall, somapacitan-beco displays non-linear pharmacokinetics, however in the clinically relevant dose range of somapacitan-beco in adults with GHD, somapacitan-beco pharmacokinetics are approximately linear. After subcutaneous administration of 0.02 – 0.16 mg/kg/week somapacitan-beco in pediatric patients with GHD, a non-linear dose-exposure relationship with a greater than dose proportional increase in exposure was observed.

Absorption

In adults with GHD, a maximum concentration of somapacitan-beco is reached 4 to 24 hours post dose.

Steady state exposure is achieved following 1 to 2 weeks of once weekly administration of subcutaneous somapacitan-beco.

In pediatric patients with GHD, maximum somapacitan-beco concentrations occurred 8 to 25 hours after dosing at doses from 0.02 mg/kg/week to 0.16 mg/kg/week and increased with increasing dose level. Steady state was achieved following 1 to 2 weekly administration.

Distribution

Somapacitan-beco is extensively bound (>99%) to plasma proteins.

Based on population PK analyses, the estimated volume of distribution (V/F) of somapacitan-beco in adult GHD patients is approximately 14.6 L and 1.7 L in pediatric patients with GHD.

Elimination

The plasma elimination half-life of somapacitan-beco is approximately 2 to 3 days in adult patients with GHD. Following a dose of 0.16 mg/kg/week, the terminal half-life of somapacitan-beco was about 34 hours in pediatric patients with GHD. Somapacitan-beco was cleared within one week after treatment discontinuation.

Metabolism: Somapacitan-beco is metabolized via proteolytic cleavage of the linker sequence between the peptide backbone and albumin binder sidechain.

Excretion: The primary excretion routes of somapacitan-beco-related material are via the urine and feces. Approximately 81% of the dose is excreted in the urine and approximately 13% is excreted in the feces. No intact somapacitan-beco is excreted indicating full breakdown of somapacitan-beco prior to excretion.

Specific Populations

Body weight: Adults with GHD -The exposure of somapacitan-beco decreases with increasing body weight. However, the somapacitan-beco dose range of 0.1 to 8 mg/week provides adequate systemic exposure to reach target IGF-1 levels over the weight range of 34.5-150.5 kg evaluated in the clinical trials.

Pediatric patients with GHD: Based on pharmacokinetic analysis, gender and race do not have a clinically meaningful effect on the pharmacokinetics. The exposure of somapacitan-beco decreases with increasing body weight. However, the somapacitan-beco dose of 0.16 mg/kg/week provides adequate systemic exposure for pediatrics to reach target IGF-1 levels over the weight range of 9.9 to 61.8 kg evaluated in the clinical trials.

Geriatric patients: Adult patients greater than 65 years of age and geriatric patients have a higher exposure than younger subjects at the same somapacitan-beco dose [see Dosage and Administration (2.5) and Use in Specific Populations (8.5)].

Female patients receiving estrogen: Female patients and in particular female patients on oral estrogen, have lower exposure than males at the same somapacitan-beco dose [see Dosage and Administration (2.5) and Drug Interactions (7)].

Hepatic impairment: A somapacitan-beco dose of 0.08 mg/kg at steady state resulted in comparable somapacitan-beco exposure between patients with normal hepatic function and mild hepatic impairment (Child-Pugh A). However, higher exposure was observed in patients with moderate hepatic impairment (Child-Pugh B) (ratios to normal hepatic function were 4.69 and 3.52-fold increase for AUC0-168h and Cmax, respectively). Lower somapacitan-beco stimulated IGF-1 levels were observed in patients with mild and moderate hepatic impairment (ratios to normal hepatic function were 0.85 and 0.75, respectively) [see Dosage and Administration (2.5) and Use in Specific Populations (8.6)].

Renal impairment: In general, somapacitan-beco exposure tended to increase with decreasing estimated glomerular filtration rate. A somapacitan-beco dose of 0.08 mg/kg at steady state resulted in higher exposures in patients with renal impairment, that was most pronounced for patients with severe renal impairment and patients requiring hemodialysis (AUC0-168h ratios to normal renal function were 1.75 and 1.63, respectively). Higher IGF-1 AUC0-168h levels were also observed in patients with moderate and severe renal impairment and in patients requiring hemodialysis (ratios to normal renal function were 1.35, 1.40 and 1.24, respectively).

12.6 Immunogenicity

The observed incidence of anti-drug antibodies is highly dependent on the sensitivity and specificity of the assay. Differences in assay methods preclude meaningful comparisons of the incidence of anti-drug antibodies in the studies described below with the incidence of anti-drug antibodies in other studies, include those of SOGROYA or other growth hormone analogs.

No anti-somapacitan-beco antibodies were detected in the clinical trials in adult patients with GHD.

Anti-somapacitan-beco binding antibodies were evaluated in samples collected at baseline, week 13, and week 52 of treatment in the 52-week main period of the phase 3 trial in pediatric patients with GHD receiving somapacitan-beco. Of the 132 subjects exposed to somapacitan-beco, 16 (12.1%) showed detectable binding antibodies to somapacitan-beco at any time during the main period of the trial following exposure to SOGROYA. 14 out of 16 subjects showed detectable binding antibodies to somapacitan-beco only at one timepoint. Of the 68 patients exposed to daily somatropin, detectable binding antibodies were detected in 7 (10.3%) children. Of these, 6 children had positive antibody samples only at one timepoint. There was no identified clinically significant effect of anti-drug antibodies on pharmacokinetics, pharmacodynamics, safety, or effectiveness of SOGROYA over the treatment duration. No neutralizing antibodies to somapacitan-beco were detected.

13 NONCLINICAL TOXICOLOGY

13.1 Carcinogenesis, Mutagenesis, Impairment of Fertility

Long term studies in animals with somapacitan-beco to evaluate carcinogenic potential have not been conducted.

Somapacitan-beco was not mutagenic or clastogenic in a standard battery of genotoxicity tests (bacterial mutagenicity (Ames), human lymphocyte chromosome aberration, rat bone marrow micronucleus).

In rat studies evaluating male and female fertility, somapacitan-beco was administered by subcutaneous injection at doses of 1, 2, and 4 mg/kg twice weekly. Males were dosed from four weeks before pairing until termination and females were dosed beginning two weeks prior to mating through gestation day 7. No adverse effects were observed on male or female fertility in rats at doses up to 4 mg/kg (29 times the MRHD, based on AUC).

14 CLINICAL STUDIES

14.1 Pediatric Patients with Growth Hormone Deficiency (GHD)

A randomized, open-label, active-controlled, parallel-group phase 3 study was conducted in 200 treatment-naïve, pediatric patients with growth hormone deficiency (GHD) (NCT03811535). The primary efficacy endpoint was annualized height velocity at Week 52.

One hundred thirty two patients (132) received 0.16 mg/kg/week SOGROYA, and 68 received 0.034 mg/kg/day daily somatropin. The patients ranged in age from 2.5 to 11 years with a mean of 6.4 years. Of these patients, 74.5% were male and 25.5% were female. Fifty-seven percent (57%) of patients were Caucasian, 37% of patients were Asian, 0.5% of patients were Black or African American, 5.0% were not reported, and 0.5% were categorized as “other.” The mean baseline height standard deviation score (SDS) of -2.99 (1.02) in SOGROYA group and -3.47 (1.52) in daily somatropin group.

Treatment with once-weekly SOGROYA for 52 weeks resulted in an annualized height velocity of 11.2 cm/year. Patients treated with daily somatropin achieved an annualized height velocity of 11.7 cm/year after 52 weeks of treatment. Refer to Table 5.

Table 5. Annualized Height Velocity at Week 52 in pediatric patients with GHD

 | Once-Weekly SOGROYA; (N=132) | Daily somatropin; (N=68) | Estimate of treatment difference (95% CI) (somapacitan-beco minus somatropin)
Annualized Height Velocity (cm/year) | 11.2 | 11.7 | -0.5 [-1.1; 0.2]

The mean increase in height SDS over the 52 week period was 1.25 and 1.30 in the once-weekly SOGROYA and daily somatropin groups, respectively.

14.2 Adults with Growth Hormone Deficiency (GHD)

In a 35-week, double-blind, placebo-controlled study, treatment-naïve adult patients with GHD were randomized (2:1:2) and exposed to once-weekly SOGROYA 10 mg/1.5mL (n=120) or placebo (n=60) or a daily somatropin product 10 mg/1.5mL (n=119) for a 34-week treatment period (NCT02229851).

In this study, patients were 51.7% female and had a mean age of 45.1 years. Most patients were 23 to 64 years old and most (69.7%) had adult onset GHD. The mean BMI was 27.4 kg/m^2. Overall, 66.7% were White, 28.7% were Asian and 2.3% were Black or African American; 4.5% identified as Hispanic or Latino ethnicity.

Treatment with SOGROYA demonstrated superiority compared to placebo in reduction in truncal fat percentage (%) as assessed by dual X-ray absorptiometry, with a change of -1.06% for SOGROYA and +0.47% for placebo after 34 weeks (see Table 6). Patients treated with daily somatropin achieved a change in truncal fat % of -2.23% after 34 weeks.

Table 6. Truncal Fat % Results for weekly SOGROYA, weekly placebo and daily somatropin during the 34-week pivotal trial

Change from baseline at 34 weeks | Weekly Placebo | Weekly SOGROYA | Daily Somatropin
Number of subjects in FAS (N) | 61 | 120 | 119
Truncal fat % (baseline) | 36.9 | 39.11 | 38.10
Truncal fat % | 0.47 | -1.06 | -2.23
Absolute Treatment Difference (%)*; [95% Confidence Interval]; p-value | -1.53; [-2.68; -0.38]; 0.0090

Abbreviations: FAS = Full analysis set, N = Number of subjects in FAS. Changes in truncal fat % from baseline to 34 weeks were analyzed using an analysis of covariance model with treatment, GHD onset type, sex, region, diabetes mellitus status and sex by region by diabetes mellitus interaction as factors and baseline as a covariate incorporating a multiple imputation technique where missing week 34 values were imputed based on data from the placebo group.
*No formal statistical comparison between SOGROYA and daily somatropin was performed.

After 34 weeks SOGROYA normalized the mean IGF-1 SDS level in treatment-naïve adult patients with GHD with a IGF-1 SDS of -0.17 in SOGROYA-treated patients compared to -2.62 in placebo-treated patients (see Table 7). The mean IGF-1 SDS levels in daily somatropin-treated patients was -2.53 at baseline and -0.23 at 34 weeks.

Table 7. IGF-1 SDS for SOGROYA compared to placebo during the 34-week pivotal trial

 | SOGROYA | Placebo
Number of subjects in FAS (N) | 120 | 61
IGF-1 SDS values at baseline, mean | -2.54 | -2.64
IGF-1 SDS value at week 34, mean | -0.17 | -2.62

Abbreviations: IGF-1 SDS: Insulin-like growth factor-1 standard deviation score, FAS = full analysis set, N = Number of patients in FAS. Baseline and end of main period (week 34) are observed means. Changes from baseline to the 35-week’s measurements were analysed using a mixed-effect model for repeated measurements including treatment, GHD onset type, sex, region, diabetes mellitus and sex by region by diabetes mellitus interaction as factors and baseline as a covariate, all nested within week as a factor.

16 HOW SUPPLIED/STORAGE AND HANDLING

How Supplied

SOGROYA (somapacitan-beco) injection is a clear to slightly opalescent and colorless to slightly yellow solution available as one 1.5 mL single-patient-use prefilled pen per carton:

- SOGROYA 5 mg/1.5 mL (3.3 mg/mL) pen (teal) NDC 0169-2035-11
- SOGROYA 10 mg/1.5 mL (6.7 mg/mL) pen (yellow) NDC 0169-2030-11
- SOGROYA 15 mg/1.5 mL (10 mg/mL) pen (red) NDC 0169-2037-11
  SOGROYA 5 mg/1.5 mL, 10 mg/1.5 mL, and 15 mg/1.5 mL pens are compatible with FlexPro® PenMate®. The FlexPro PenMate is an accessory device that is dispensed separately with its enclosed Instructions for Use.

Storage and Handling

Before and during use: Store in a refrigerator at 36°F to 46°F (2°C to 8°C) with the cap on and in the original carton to protect from light. Do not freeze. Do not use SOGROYA if it has been frozen. Discard prefilled pen if kept above 86°F (30°C). Avoid direct or excessive heat. Avoid sunlight. Refer to storage conditions for SOGROYA (Table 8).

Write the date of first use in the space provided on the carton.

Always remove and safely discard the needle after each injection and store the SOGROYA prefilled pen without an injection needle attached. Always use a new needle for each injection to prevent contamination.

Table 8. Storage conditions for SOGROYA

 | Before first use (unopened) |  | After first use (opened)
 | Refrigerated; 36°F to 46°F; (2°C to 8°C) | Room Temperature; up to 77°F (25°C) | Refrigerated; 36°F to 46°F; (2°C to 8°C) | Room Temperature; up to 77°F (25°C)
SOGROYA | Until expiration date | Maximum 72 hours (3 days)* | up to 6 weeks | Maximum 72 hours (3 days)*

*The total time allowed at room temperature (up to 77°F [25°C]) is 72 hours (3 days) regardless of whether the product is in-use (opened) or before first use (unopened). Must discard if kept above 86°F (30°C).

17 PATIENT COUNSELING INFORMATION

Advise patients and/or caregivers to read the FDA-approved patient labeling (Patient Information and Instructions for Use).

- Advise patients and/or caregivers to administer SOGROYA once weekly.
- Hypersensitivity - Advise patients and/or caregivers that severe and/or serious systemic hypersensitivity reactions (anaphylaxis and angioedema) have been reported, and to seek prompt medical attention should an allergic reaction occur [see Warnings and Precautions (5.2)].
- Neoplasms – Advise patients to report marked changes in skin pigmentation or changes in the appearance of preexisting nevi.
- Glucose Intolerance/ Diabetes Mellitus – Advise patients that new onset pre- /diabetes mellitus or exacerbation of preexisting diabetes mellitus can occur and monitoring of blood glucose during treatment with SOGROYA may be needed.
- Intracranial Hypertension - Advise patients to report to their healthcare provider any visual changes, headache, and nausea and/or vomiting.
- Fluid Retention - Advise patients that fluid retention during SOGROYA replacement therapy may frequently occur. Inform patients of the clinical manifestations of fluid retention (e.g. edema, arthralgia, myalgia, nerve compression syndromes including carpal tunnel syndrome/paresthesia) and to report to their healthcare provider any of these signs or symptoms occur during treatment with SOGROYA.
- Hypoadrenalism - Advise patients who have or who are at risk for corticotropin deficiency that hypoadrenalism may develop and to report to their healthcare provider if they experience hyperpigmentation, extreme fatigue, dizziness, weakness, or weight loss.
- Hypothyroidism - Advise patients/caregivers that undiagnosed/untreated hypothyroidism may prevent an optimal response to SOGROYA. Advise patients/caregivers they may require periodic thyroid function tests.
- Pancreatitis - Advise patients that pancreatitis may develop and to report to their healthcare provider any new onset abdominal pain.
- Lipohypertrophy/ Lipoatrophy – Advise patients that lipohypertrophy or lipoatrophy can occur if SOGROYA is administered subcutaneously at the same site over a long period of time. Advise patients to rotate injection sites when administering SOGROYA to reduce this risk.

Novo Nordisk® and PenMate® are registered trademarks of Novo Nordisk A/S.

SOGROYA® and FlexPro® are registered trademarks of Novo Nordisk Health Care AG.

© 2025 Novo Nordisk Health Care AG

PATENT INFORMATION: http://novonordisk-us.com/products/product-patents.html

For information about SOGROYA contact:

Novo Nordisk Inc.

800 Scudders Mill Road

Plainsboro, New Jersey 08536

1-888-668-6444

Manufactured by:

Novo Nordisk Inc.

800 Scudders Mill Road

Plainsboro, NJ 08536

U.S. License No. 1261

PATIENT INFORMATION

SOGROYA® (suh-GROY-uh)

(somapacitan-beco) injection, for subcutaneous use

What is SOGROYA?

- SOGROYA is a prescription medicine that contains human growth hormone, the same growth hormone made by the human body.
- SOGROYA is given by injection under the skin (subcutaneous) and is used to treat adults and children 2.5 years and older who do not make enough growth hormone.

Do not use SOGROYA if:

- you have a critical illness caused by certain types of heart or stomach surgery, trauma or breathing (respiratory) problems.
- you have cancer or other tumors.
- you are allergic to somapacitan-beco or any of the ingredients in SOGROYA. See the end of this Patient Information leaflet for a complete list of ingredients in SOGROYA.
- your healthcare provider tells you that you have certain types of eye problems caused by diabetes (diabetic retinopathy).
- you are a child with closed bone growth plates.
- you are a child with Prader-Willi syndrome who is severely obese or has breathing problems including sleep apnea (briefly stop breathing during sleep).

Before taking SOGROYA, tell your healthcare provider about all of your medical conditions, including if you:

- have had heart or stomach surgery, trauma or serious breathing (respiratory) problems.
- have had cancer or any tumor.
- have diabetes.
- have adrenal gland problems.
- are taking replacement therapy with glucocorticoids.
- have thyroid gland problems.
- have liver problems.
- are a child with a history of worsening of curvature of the spine (scoliosis).
- are pregnant or plan to become pregnant. It is not known if SOGROYA will harm your unborn baby. Talk to your healthcare provider if you are pregnant or plan to become pregnant.
- are breastfeeding or plan to breastfeed. It is not known if SOGROYA passes into your breast milk. You and your healthcare provider should decide if you will take SOGROYA while you breastfeed.

Tell your healthcare provider about all the medicines you take, including prescription and over-the-counter medicines, vitamins, and herbal supplements. SOGROYA may affect how other medicines work, and other medicines may affect how SOGROYA works.

How should I use SOGROYA?

- Read the detailed Instructions for Use that come with SOGROYA.
- SOGROYA comes in 3 strengths: 5 mg/1.5 mL (3.3 mg/mL) pen, 10 mg/1.5 mL (6.7 mg/mL) pen, and 15 mg/1.5 mL (10 mg/mL) pen. Your healthcare provider will prescribe the dose that is right for you.
- Your healthcare provider will show you how to inject SOGROYA.
- Use SOGROYA exactly as your healthcare provider tells you to.
- Use SOGROYA 1 time each week.
- If you miss a dose of SOGROYA, the missed dose can be taken within 3 days (72 hours) after the scheduled dosing day. One-time weekly dosing for the next dose can be started again on the regularly scheduled dosing day.
- If more than 3 days (72 hours) have passed, skip the missed dose and take your next dose on the regularly scheduled dosing day.
  - SOGROYA pens are for use by 1 person only.
  - Do not share your SOGROYA pens and needles with another person, even if the needle has been changed. You may give another person an infection or get an infection from them.

What are the possible side effects of SOGROYA?

SOGROYA may cause serious side effects, including:

- high risk of death in people who have critical illnesses because of heart or stomach surgery, trauma, or serious breathing (respiratory) problems.
- increased risk of growth of cancer or a tumor that is already present and increased risk of the return of cancer or a tumor in people who were treated with radiation to the brain or head as children and who developed low growth hormone problems. Your or your child’s healthcare provider will need to monitor you or your child for a return of cancer or a tumor. Contact the healthcare provider if you or your child start to have sudden changes in behavior, headaches, vision problems, or changes in moles, birthmarks, or the color of your or your child’s skin.
- new or worsening high blood sugar (hyperglycemia) or diabetes. You or your child’s blood sugar may need to be monitored during treatment with SOGROYA.
- increase in pressure in the skull (intracranial hypertension). If you or your child have headaches, eye problems, nausea or vomiting, contact the healthcare provider.
- serious allergic reactions. Get medical help right away if you or your child have the following symptoms:

- swelling of your face, lips, mouth, or tongue
- trouble breathing
- wheezing
- severe itching

- skin rashes, redness, or swelling
- dizziness or fainting
- fast heartbeat or pounding in your chest
- sweating

- your or your child’s body holding too much fluid (fluid retention) such as swelling in the hands and feet, pain in your or your child’s joints or muscles or nerve problems that cause pain, burning or tingling in the hands, arms, legs and feet. Tell your or your child’s healthcare provider if you or your child have any of these signs or symptoms of fluid retention.
- decrease in a hormone called cortisol. The healthcare provider will do blood tests to check your or your child’s cortisol levels. Tell your or your child’s healthcare provider if you or your child has darkening of the skin, severe fatigue, dizziness, weakness, or weight loss.
- decrease in thyroid hormone levels. Decreased thyroid hormone levels may affect how well SOGROYA works. The healthcare provider will do blood tests to check your or your child’s thyroid hormone levels.
- severe and constant abdominal pain. This could be a sign of pancreatitis. Tell your or your child’s healthcare provider if you or your child has any new abdominal pain.
- loss of fat and tissue weakness in the area of skin you or your child inject. Talk to your or your child’s healthcare provider about rotating the areas where you or your child inject SOGROYA.
- worsening of curvature of the spine in children (scoliosis).
- hip and knee pain or a limp in children (slipped capital femoral epiphysis). This may lead to a serious condition where bone tissue dies due to a lack of blood supply (osteonecrosis). Get medical help right away if you or your child develops a limp or has hip or knee pain.
- high risk of sudden death in children with Prader-Willi syndrome who are severely obese or have breathing problems, including sleep apnea. See “Do not use SOGROYA if”.
- increase in phosphorus, alkaline phosphatase, and parathyroid hormone levels in your blood. Your or your child’s healthcare provider will do blood tests to check this.

The most common side effects of SOGROYA in children include:

- common cold
- headache
- fever

- pain in extremity
- reaction to injection

The most common side effects of SOGROYA in adults include:

- back pain
- joint pain
- indigestion
- sleep problems
- dizziness
- swelling of the tonsils (tonsillitis)

- vomiting
- high blood pressure
- increase in the level of an enzyme in your blood called creatine phosphokinase
- weight gain
- low red blood cells (anemia)

These are not all the possible side effects of SOGROYA.

Call your doctor for medical advice about side effects. You may report side effects to FDA at 1-800-FDA-1088.

You may also report side effects to Novo Nordisk at 1-888-668-6444.

How should I store SOGROYA?

- Before you use SOGROYA pens for the first time:
- Store your new, unused SOGROYA pen in a refrigerator between 36ºF to 46ºF (2ºC to 8ºC).
- Store your new, unused SOGROYA pen with the cap on and keep it in the original carton.
- Do not freeze SOGROYA.
- Keep SOGROYA away from direct heat and light.
- Do not use SOGROYA that has been frozen or in temperatures warmer than 86ºF (30ºC).
- Do not use SOGROYA after the expiration date printed on the carton and the pen.
- After you use SOGROYA pens and there is still medicine left:
- Store remaining SOGROYA in the refrigerator between 36ºF to 46ºF (2ºC to 8ºC) and use within 6 weeks.
- Store your in-use SOGROYA pen with the cap on and keep it in the original carton.
- If needed, unused and in-use SOGROYA pens can be stored out of the refrigerator. SOGROYA pens can be stored at room temperature no warmer than 77ºF (25ºC) for up to 3 days (72 hours) and then returned to the refrigerator.

Keep SOGROYA and all medicines out of the reach of children.

General information about the safe and effective use of SOGROYA.

Medicines are sometimes prescribed for purposes other than those listed in a Patient Information leaflet. Do not use SOGROYA for a condition for which it was not prescribed. Do not give SOGROYA to other people, even if they have the same symptoms that you have. It may harm them. You can ask your pharmacist or healthcare provider for information about SOGROYA that is written for health professionals.

What are the ingredients in SOGROYA?

Active ingredient: somapacitan-beco

Inactive ingredients: histidine, mannitol, phenol, poloxamer 188, Water for Injection, and hydrochloric acid and sodium hydroxide (as needed)

Manufactured by: Novo Nordisk Inc., Plainsboro, NJ 08536

This Patient Information has been approved by the U.S. Food and Drug Administration. Revised: 07/2025

Instructions for Use – 5 mg/1.5 mL (3.3 mg/mL)

Instructions for Use

SOGROYA® 5 mg

(suh-GROY-uh)

(somapacitan-beco) injection

5 mg/1.5 mL (3.3 mg/mL)

Supplies you will need:

- SOGROYA prefilled Pen
- new injection needle. SOGROYA prefilled Pen is designed to be used with all Novo Nordisk disposable needles up to a length of 8 mm.
- sharps disposal container. See Step 5 for information on how to throw away (dispose of) used needles and Pens.
- alcohol pad
- gauze pad

How to use your SOGROYA Pen

5 steps you should follow for a SOGROYA injection:

Step 1: Prepare your SOGROYA Pen

Step 2: Check the SOGROYA flow with each new Pen

Step 3: Select your dose

Step 4: Inject your dose

Step 5: After your injection

For further information about your Pen see: Frequently Asked Questions and

Important information

Important information

Pay special attention to these notes as they are important for safe use of the Pen.

Additional information

SOGROYA is a prefilled growth hormone Pen. It contains 5 mg of somapacitan-beco and delivers doses from 0.025 mg to 2.0 mg, in increments of 0.025 mg. SOGROYA is for use under the skin only (subcutaneous) for injection 1 time each week.

Do not share your SOGROYA Pen and needles with another person. You may give another person an infection or get an infection from them.

Do not use your Pen without proper training from your healthcare provider. Make sure that you are confident in giving an injection with the Pen before you start your treatment. If you are blind or have poor eyesight and cannot read the dose counter on the Pen, do not use this Pen without help. Get help from a person with good eyesight who is trained to use the Pen.

Step 1. Prepare your SOGROYA Pen

- Wash your hands with soap and water.
- Check the name, strength, and colored label on your Pen to make sure that it contains SOGROYA in the right strength.
- Pull off the Pen cap.
- Turn the Pen upside down 1 or 2 times to check that the SOGROYA in your Pen is clear to almost clear and colorless to slightly yellow (See Figure A). If SOGROYA looks cloudy or you see particles, do not use the Pen.

- When you are ready to give your injection, get a new disposable needle, and remove the paper tab.
- Push the needle straight onto the Pen. Turn the needle clockwise until it is on tight (See Figure B).

Make sure the right pen is used. Especially if you use more than one type of injection medicine. Using the wrong medicine could be harmful to your health.

Always use a new needle for each injection. This reduces the risk of contamination, infection, leakage of SOGROYA, and blocked needles leading to incorrect dosing.

- Pull off the outer needle cap and throw it away (dispose of) (See Figure C).

- Pull off the inner needle cap and throw it away (dispose of) (See Figure D).

A drop of SOGROYA may appear at the needle tip. This is normal, but you must still check the SOGROYA flow with each new Pen (See Step 2).

Never use a bent or damaged needle.

Step 2. Check the SOGROYA flow with each new Pen

If your Pen is already in use, go to Step 3.

- Before using a new Pen, check the SOGROYA flow to make sure the growth hormone can flow through the Pen and needle.
- Turn the dose selector clockwise 1 marking on the dose counter to select 0.025 mg. You may hear a faint “click” when you turn the dose selector (See Figure E).

- 1 marking on the dose counter equals 0.025 mg (See Figure F).

- Hold the Pen with the needle pointing up. Press and hold in the dose button until the dose counter returns to “0”. The “0” must line up with the dose pointer (See Figure G).

- Check that a drop of SOGROYA appears at the needle tip (See Figure H).

If no SOGROYA appears, repeat Step 2 up to 6 times.

If you still do not see a drop of SOGROYA, change the needle:

- Carefully remove the needle from the Pen by turning the needle counterclockwise. Place the needle in a sharps disposal container immediately (See Step 5).
- Repeat Step 2 again.

Do not use the Pen if a drop of SOGROYA still does not appear after changing the needle and repeating Step 2. Call Novo Nordisk at 1-888-668-6444 for help.

Step 3. Select your dose

- To start, check that the dose pointer is set at “0”.
- Turn the dose selector clockwise to select the dose you need (See Figure I). When you have selected your dose, you can go to Step 4.

If there is not enough SOGROYA left to select a full dose, see Frequently Asked Questions.

The dose counter shows the dose in “mg” (See Figure J and Figure K). Always use the dose counter to select the exact dose. Do not use the “click” sounds you hear when you turn the dose selector to select your dose. Only the dose pointer on the dose counter will show the exact dose selected.

If you select the wrong dose, you can turn the dose selector clockwise or counterclockwise to the correct dose (See Figure L).

The Pen “clicks” sound and feel differently when the dose selector is turned clockwise, counterclockwise, or if you forcefully move it past the number of “mg” left in the Pen.

Step 4. Inject your dose

- Select the injection site.
- SOGROYA can be injected under the skin (subcutaneously) of your stomach area (abdomen) or upper legs (thighs) as instructed by your healthcare provider (See Figure M). Change the injection site every week.
- Wipe the injection site with an alcohol pad and let the area dry.
- Insert the needle into your skin as your healthcare provider has shown you (See Figure N).
- Make sure you can see the dose counter. Do not cover it with your fingers. This could block the injection.

- Press and hold down the dose button until the dose counter shows “0” (See Figure O). The “0” must line up with the dose pointer. You may then hear or feel a “click”.
- Continue to hold down the dose button with the needle in your skin.

If “0” does not appear in the dose

counter after continuously pressing the dose button, your needle may be blocked or damaged. See Frequently Asked Questions.

- Keep holding down the dose button with the needle in your skin andslowly count to 6 to make sure that the full dose has been delivered (See Figure P).

- Carefully remove the needle from your skin (See Figure Q). If blood appears at the injection site, press lightly with a gauze pad. Do not rub the area.

You may see a drop of SOGROYA at the needle tip after injecting. This is normal and does not affect your dose.

Step 5. After your injection

- Carefully remove the needle from the Pen by turning the needle counterclockwise (See Figure R).
- Place the needle in an FDA-cleared sharps disposal container immediately to reduce the risk of a needle stick (See Figure R).

Always throw away (dispose of) the needle after each injection.

For further information about safe sharps disposal, see Frequently Asked Questions.

- Put the Pen cap on your Pen after each use to protect SOGROYA from direct light (See Figure S).
See “How should I store my SOGROYA Pen?”.

Do not try to put the needle cap back on. You may stick yourself with the needle.

Always remove the needle from your Pen immediately after each injection. This reduces the risk of contamination, infection, leakage of SOGROYA, and blocked needles leading to incorrect dosing.

How should I store my SOGROYA Pen?

                        Before you use SOGROYA Pen for the first time:
- Store your new, unused SOGROYA Pen in a refrigerator between 36°F to 46°F (2°C to 8°C).
- Store your new, unused SOGROYA Pen with the cap on and in the original carton.
- Do not freeze SOGROYA.
- When stored in the refrigerator, do not store the SOGROYA Pen directly next to the cooling element.
- Keep SOGROYA away from direct heat and light.
- Do not use SOGROYA if it has been frozen or in temperatures warmer than 86ºF (30°C).
- Do not use SOGROYA after the expiration date printed on the carton and the Pen.
                        After you use SOGROYA Pen and there is still medicine left:
- Store remaining SOGROYA in the refrigerator between 36°F to 46°F (2°C to 8°C) and use within 6 weeks.
- Store your in-use SOGROYA Pen with the cap on and keep it in the original carton.

Do not store SOGROYA Pen with the needle attached.

If needed, unused and in-use SOGROYA pens can be stored out of the refrigerator. SOGROYA pens can be stored at room temperature no warmer than 77ºF (25ºC) for up to 3 days (72 hours) and then returned to the refrigerator. Throw away (dispose of) SOGROYA if it has been stored above 77°F (25°C) for more than 3 days (72 hours) or in temperatures warmer than 86°F (30°C).

Always keep your SOGROYA Pen and needles out of reach of others, especially children.

Frequently Asked Questions

How do I see how much SOGROYA is left in my Pen?

The Pen scale shows you approximately how much SOGROYA is left in your Pen (See Figure T).

To see how much SOGROYA is left in your Pen, use the dose counter:

Turn the dose selector clockwise until the dose counter stops. The dose pointer will line up with the number of “mg” left in the Pen. You can select a maximum dose of 2.0 mg. If the dose counter stops with the dose pointer lined up with “2”, at least 2.0 mg are left in your Pen.

If the dose counter stops with the dose pointer lined up with “1.7”, only 1.7 mg are left in your Pen (See Figure U).

What if I need a larger dose than what is left in my Pen?

It is not possible to select a larger dose on the dose counter than the number of “mg” left in your Pen. If you need more SOGROYA than you have left in your Pen, you can use a new Pen or split your dose between your current Pen and a new Pen. Only split your dose if you have been trained or advised by your healthcare provider on how to do this. You may find it helpful to use a calculator to plan the doses as instructed by your healthcare provider.

Be very careful to calculate your split dose correctly so that you do not give the wrong dose. If you are not sure how to split your dose using 2 Pens, then select and inject the dose you need with a new Pen.

What if no SOGROYA appears when I check the flow?

A. Your needle may be blocked or damaged, if no SOGROYA appears at the needle tip. Remove the needle as described in Step 5 and repeat Step 1 and Step 2.

B. Your Pen may be defective, if SOGROYA still does not appear after changing the needle. Do not use the Pen. Contact Novo Nordisk at 1-888-668-6444.

What if “0” does not appear after completing my injection?

The needle may be blocked or damaged, and you have not received any SOGROYA,even though the dose counter has moved from the dose that you have set. Remove the needle as described in Step 5 and repeat Step 1 to Step 4.

How should I take care of my Pen?

Be careful not to drop your Pen or knock it against hard surfaces. Do not expose your Pen to dust, dirt, liquid, or direct light. See “How should I store SOGROYA?” Do not try to refill your Pen, it is prefilled.

What if I drop my Pen?

If you drop your Pen or think that something is wrong with it, attach a new disposable needle and check the SOGROYA flow before you inject (See Step 1 and Step 2). Do not try to repair your Pen or pull it apart.

How do I clean my Pen?

Do not wash, soak, or lubricate your Pen. If necessary, clean it with mild detergent on a moistened cloth.

Frequently Asked Questions

How do I throw away (dispose of) used SOGROYAneedles and Pens?

Put your used needles and Pens in an FDA-cleared sharps disposal container right away after use. Do not throw away (dispose of) loose needles and Pens in your household trash. If you do not have an FDA-cleared sharps disposal container, you may use a household container that is:

- made of a heavy-duty plastic,
- can be closed with a tight-fitting, puncture-resistant lid, without sharps being able to come out,
- upright and stable during use,
- leak-resistant, and
- properly labeled to warn of hazardous waste inside the container.

When your sharps disposal container is almost full, you will need to follow your community guidelines for the right way to dispose of your sharps disposal container. There may be state or local laws about how you should dispose of used needles and Pens. For more information about safe sharps disposal, and for specific information about safe sharps disposal in the state that you live in, go to the FDA’s website at:

http://www.fda.gov/safesharpsdisposal.

Do not dispose of your used sharps disposal container in your household trash unless your community guidelines permit this. Do not recycle your used sharps disposal container.

Important information

- Caregivers must be very careful when handling needles to reduce the risk of needle sticks and infection.

PATENT Information: http://novonordisk-us.com/products/product-patents.html

SOGROYA® is a registered trademark of Novo Nordisk Health Care AG.

Novo Nordisk® is a registered trademark of Novo Nordisk A/S.

© 2004-2023 Novo Nordisk Health Care AG

For further information contact:

Novo Nordisk Inc.

800 Scudders Mill Road

Plainsboro, NJ 08536, USA

1-888-668-6444

Sogroya.com

Manufactured by:

Novo Nordisk Inc.

Plainsboro, NJ 08536

U.S. License No. 1261

This Instructions for Use has been approved by the U.S. Food and Drug Administration.

Issued: 10/2021

Version: 1

Instructions for Use – 10 mg/1.5 mL (6.7 mg/mL)

Instructions for Use

SOGROYA® 10 mg

(suh-GROY-uh)

(somapacitan-beco) injection

10 mg/1.5 mL (6.7 mg/mL)

Supplies you will need:

- SOGROYA prefilled Pen
- new injection needle. SOGROYA prefilled Pen is designed to be used with all Novo Nordisk disposable needles up to a length of 8 mm.
- sharps disposal container. See Step 5 for information on how to throw away (dispose of) used needles and Pens.
- alcohol pad
- gauze pad

How to use your SOGROYA Pen

5 steps you should follow for a SOGROYA injection:

Step 1: Prepare your SOGROYA Pen

Step 2: Check the SOGROYA flow with each new Pen

Step 3: Select your dose

Step 4: Inject your dose

Step 5: After your injection

For further information about your Pen see: Frequently Asked Questions and

Important information

Important information

Pay special attention to these notes as they are important for safe use of the Pen.

Additional information

SOGROYA is a prefilled growth hormone Pen. It contains 10 mg of somapacitan-beco and delivers doses from 0.05 mg to 4.0 mg, in increments of 0.05 mg. SOGROYA is for use under the skin only (subcutaneous) for injection 1 time each week.

Do not share your SOGROYA Pen and needles with another person. You may give another person an infection or get an infection from them.

Do not use your Pen without proper training from your healthcare provider. Make sure that you are confident in giving an injection with the Pen before you start your treatment. If you are blind or have poor eyesight and cannot read the dose counter on the Pen, do not use this Pen without help. Get help from a person with good eyesight who is trained to use the Pen.

Step 1. Prepare your SOGROYA Pen

- Wash your hands with soap and water.
- Check the name, strength, and colored label on your Pen to make sure that it contains SOGROYA in the right strength.
- Pull off the Pen cap.
- Turn the Pen upside down 1 or 2 times to check that the SOGROYA in your Pen is clear to almost clear and colorless to slightly yellow (See Figure A). If SOGROYA looks cloudy or you see particles, do not use the Pen.

- When you are ready to give your injection, get a new disposable needle, and remove the paper tab.
- Push the needle straight onto the Pen. Turn the needle clockwise until it is on tight (See Figure B).

Make sure the right pen is used. Especially if you use more than one type of injection medicine. Using the wrong medicine could be harmful to your health.

Always use a new needle for each injection. This reduces the risk of contamination, infection, leakage of SOGROYA, and blocked needles leading to incorrect dosing.

- Pull off the outer needle cap and throw it away (dispose of) (See Figure C).

- Pull off the inner needle cap and throw it away (dispose of) (See Figure D).

A drop of SOGROYA may appear at the needle tip. This is normal, but you must still check the SOGROYA flow with each new Pen (See Step 2).

Never use a bent or damaged needle.

Step 2. Check the SOGROYA flow with each new Pen

If your Pen is already in use, go to Step 3.

- Before using a new Pen, check the SOGROYA flow to make sure the growth hormone can flow through the Pen and needle.
- Turn the dose selector clockwise 1 marking on the dose counter to select 0.05 mg. You may hear a faint “click” when you turn the dose selector (See Figure E).

- 1 marking on the dose counter equals 0.05 mg (See Figure F).

- Hold the Pen with the needle pointing up. Press and hold in the dose button until the dose counter returns to “0”. The “0” must line up with the dose pointer (See Figure G).

- Check that a drop of SOGROYA appears at the needle tip (See Figure H).

If no SOGROYA appears, repeat Step 2 up to 6 times.

If you still do not see a drop of SOGROYA, change the needle:

- Carefully remove the needle from the Pen by turning the needle counterclockwise. Place the needle in a sharps disposal container immediately (See Step 5).
- Repeat Step 2 again.

Do not use the Pen if a drop of SOGROYA still does not appear after changing the needle and repeating Step 2. Call Novo Nordisk at 1-888-668-6444 for help.

Step 3. Select your dose

- To start, check that the dose pointer is set at “0”.
- Turn the dose selector clockwise to select the dose you need (See Figure I). When you have selected your dose, you can go to Step 4.

If there is not enough SOGROYA left to select a full dose, see Frequently Asked Questions.

The dose counter shows the dose in “mg” (See Figure J and Figure K). Always use the dose counter to select the exact dose. Do not use the “click” sounds you hear when you turn the dose selector to select your dose. Only the dose pointer on the dose counter will show the exact dose selected.

If you select the wrong dose, you can turn the dose selector clockwise or counterclockwise to the correct dose (See Figure L).

The Pen “clicks” sound and feel differently when the dose selector is turned clockwise, counterclockwise, or if you forcefully move it past the number of “mg” left in the Pen.

Step 4. Inject your dose

- Select the injection site.
- SOGROYA can be injected under the skin (subcutaneously) of your stomach area (abdomen) or upper legs (thighs) as instructed by your healthcare provider (See Figure M). Change the injection site every week.
- Wipe the injection site with an alcohol pad and let the area dry.
- Insert the needle into your skin as your healthcare provider has shown you (See Figure N).
- Make sure you can see the dose counter. Do not cover it with your fingers. This could block the injection.

- Press and hold down the dose button until the dose counter shows “0” (See Figure O). The “0” must line up with the dose pointer. You may then hear or feel a “click”.
- Continue to hold down the dose button with the needle in your skin.

If “0” does not appear in the dose counter after continuously pressing the dose button, your needle may be blocked or damaged. See Frequently Asked Questions.

- Keep holding down the dose button with the needle in your skinand slowly count to 6 to make sure that the full dose has been delivered (See Figure P).

- Carefully remove the needle from your skin (See Figure Q). If blood appears at the injection site, press lightly with a gauze pad. Do not rub the area.

You may see a drop of SOGROYA at the needle tip after injecting. This is normal and does not affect your dose.

Step 5. After your injection

- Carefully remove the needle from the Pen by turning the needle counterclockwise (See Figure R).
- Place the needle in an FDA-cleared sharps disposal container immediately to reduce the risk of a needle stick (See Figure R).

Always throw away (dispose of) the needle after each injection.

For further information about safe sharps disposal, see Frequently Asked Questions.

- Put the Pen cap on your Pen after each use to protect SOGROYA from direct light (See Figure S).
See “How should I store my SOGROYA Pen?”.

Do not try to put the needle cap back on. You may stick yourself with the needle.

Always remove the needle from your Pen immediately after each injection. This reduces the risk of contamination, infection, leakage of SOGROYA, and blocked needles leading to incorrect dosing.

How should I store my SOGROYA Pen?

                        Before you use SOGROYA Pen for the first time:
- Store your new, unused SOGROYA Pen in a refrigerator between 36°F to 46°F (2°C to 8°C).
- Store your new, unused SOGROYA Pen with the cap on and in the original carton.
- Do not freeze SOGROYA.
- When stored in the refrigerator, do not store the SOGROYA Pen directly next to the cooling element.
- Keep SOGROYA away from direct heat and light.
- Do not use SOGROYA if it has been frozen or in temperatures warmer than 86ºF (30°C).
- Do not use SOGROYA after the expiration date printed on the carton and the Pen.
                        After you use SOGROYA Pen and there is still medicine left:
- Store remaining SOGROYA in the refrigerator between 36°F to 46°F (2°C to 8°C) and use within 6 weeks.
- Store your in-use SOGROYA Pen with the cap on and keep it in the original carton.

Do not store SOGROYA Pen with the needle attached.

If needed, unused and in-use SOGROYA pens can be stored out of the refrigerator. SOGROYA pens can be stored at room temperature no warmer than 77ºF (25ºC) for up to 3 days (72 hours) and then returned to the refrigerator. Throw away (dispose of) SOGROYA if it has been stored above 77°F (25°C) for more than 3 days (72 hours) or in temperatures warmer than 86°F (30°C).

Always keep your SOGROYA Pen and needles out of reach of others, especially children.

Frequently Asked Questions

How do I see how much SOGROYA is left in my Pen?

The Pen scale shows you approximately how much SOGROYA is left in your Pen (See Figure T).

To see how much SOGROYA is left in your Pen, use the dose counter:

Turn the dose selector clockwise until the dose counter stops. The dose pointer will line up with the number of “mg” left in the Pen. You can select a maximum dose of 4.0 mg. If the dose counter stops with the dose pointer lined up with “4”, at least 4.0 mg are left in your Pen.

If the dose counter stops with the dose pointer lined up with “2.8”, only 2.8 mg are left in your Pen (See Figure U).

What if I need a larger dose than what is left in my Pen?

It is not possible to select a larger dose on the dose counter than the number of “mg” left in your Pen. If you need more SOGROYA than you have left in your Pen, you can use a new Pen or split your dose between your current Pen and a new Pen. Only split your dose if you have been trained or advised by your healthcare provider on how to do this. You may find it helpful to use a calculator to plan the doses as instructed by your healthcare provider.

Be very careful to calculate your split dose correctly so that you do not give the wrong dose. If you are not sure how to split your dose using 2 Pens, then select and inject the dose you need with a new Pen.

What if no SOGROYA appears when I check the flow?

A. Your needle may be blocked or damaged, if no SOGROYA appears at the needle tip. Remove the needle as described in Step 5 and repeat Step 1 and Step 2.

B. Your Pen may be defective, if SOGROYA still does not appear after changing the needle. Do not use the Pen. Contact Novo Nordisk at 1-888-668-6444.

What if “0” does not appear after completing my injection?

The needle may be blocked or damaged, and you have not received any SOGROYA,even though the dose counter has moved from the dose that you have set. Remove the needle as described in Step 5 and repeat Step 1 to Step 4.

How should I take care of my Pen?

Be careful not to drop your Pen or knock it against hard surfaces. Do not expose your Pen to dust, dirt, liquid, or direct light. See “How should I store SOGROYA?” Do not try to refill your Pen, it is prefilled.

What if I drop my Pen?

If you drop your Pen or think that something is wrong with it, attach a new disposable needle and check the SOGROYA flow before you inject (See Step 1 and Step 2). Do not try to repair your Pen or pull it apart.

How do I clean my Pen?

Do not wash, soak, or lubricate your Pen. If necessary, clean it with mild detergent on a moistened cloth.

Frequently Asked Questions

How do I throw away (dispose of) used SOGROYAneedles and Pens?

Put your used needles and Pens in an FDA-cleared sharps disposal container right away after use. Do not throw away (dispose of) loose needles and Pens in your household trash. If you do not have an FDA-cleared sharps disposal container, you may use a household container that is:

- made of a heavy-duty plastic,
- can be closed with a tight-fitting, puncture-resistant lid, without sharps being able to come out,
- upright and stable during use,
- leak-resistant, and
- properly labeled to warn of hazardous waste inside the container.

When your sharps disposal container is almost full, you will need to follow your community guidelines for the right way to dispose of your sharps disposal container. There may be state or local laws about how you should dispose of used needles and Pens. For more information about safe sharps disposal, and for specific information about safe sharps disposal in the state that you live in, go to the FDA’s website at:

http://www.fda.gov/safesharpsdisposal.

Do not dispose of your used sharps disposal container in your household trash unless your community guidelines permit this. Do not recycle your used sharps disposal container.

Important information

- Caregivers must be very careful when handling needles to reduce the risk of needle sticks and infection.

PATENT Information: http://novonordisk-us.com/products/product-patents.html

SOGROYA® is a registered trademark of Novo Nordisk Health Care AG.

Novo Nordisk® is a registered trademark of Novo Nordisk A/S.

© 2004-2023 Novo Nordisk Health Care AG

For further information contact:

Novo Nordisk Inc.

800 Scudders Mill Road

Plainsboro, NJ 08536, USA

1-888-668-6444

Sogroya.com

Manufactured by:

Novo Nordisk Inc.

Plainsboro, NJ 08536

U.S. License No. 1261

This Instructions for Use has been approved by the U.S. Food and Drug Administration.

Revised: 10/2021

Version: 2

Instructions for Use – 15 mg/1.5 mL (10 mg/mL)

Instructions for Use

SOGROYA® 15 mg

(suh-GROY-uh)

(somapacitan-beco) injection

15 mg/1.5 mL (10 mg/mL)

Supplies you will need:

- SOGROYA prefilled Pen
- new injection needle. SOGROYA prefilled Pen is designed to be used with all Novo Nordisk disposable needles up to a length of 8 mm.
- sharps disposal container. See Step 5 for information on how to throw away (dispose of) used needles and Pens.
- alcohol pad
- gauze pad

How to use your SOGROYA Pen

5 steps you should follow for a SOGROYA injection:

Step 1: Prepare your SOGROYA Pen

Step 2: Check the SOGROYA flow with each new Pen

Step 3: Select your dose

Step 4: Inject your dose

Step 5: After your injection

For further information about your Pen see: Frequently Asked Questions and

Important information

Important information

Pay special attention to these notes as they are important for safe use of the Pen.

Additional information

SOGROYA is a prefilled growth hormone Pen. It contains 15 mg of somapacitan-beco and delivers doses from 0.1 mg to 8.0 mg, in increments of 0.1 mg. SOGROYA is for use under the skin only (subcutaneous) for injection 1 time each week.

Do not share your SOGROYA Pen and needles with another person. You may give another person an infection or get an infection from them.

Do not use your Pen without proper training from your healthcare provider. Make sure that you are confident in giving an injection with the Pen before you start your treatment. If you are blind or have poor eyesight and cannot read the dose counter on the Pen, do not use this Pen without help. Get help from a person with good eyesight who is trained to use the Pen.

Step 1. Prepare your SOGROYA Pen

- Wash your hands with soap and water.
- Check the name, strength, and colored label on your Pen to make sure that it contains SOGROYA in the right strength.
- Pull off the Pen cap.
- Turn the Pen upside down 1 or 2 times to check that the SOGROYA in your Pen is clear to almost clear and colorless to slightly yellow (See Figure A). If SOGROYA looks cloudy or you see particles, do not use the Pen.

- When you are ready to give your injection, get a new disposable needle, and remove the paper tab.
- Push the needle straight onto the Pen. Turn the needle clockwise until it is on tight (See Figure B).

Make sure the right pen is used. Especially if you use more than one type of injection medicine. Using the wrong medicine could be harmful to your health.

Always use a new needle for each injection. This reduces the risk of contamination, infection, leakage of SOGROYA, and blocked needles leading to incorrect dosing.

- Pull off the outer needle cap and throw it away (dispose of) (See Figure C).

- Pull off the inner needle cap and throw it away (dispose of) (See Figure D).

A drop of SOGROYA may appear at the needle tip. This is normal, but you must still check the SOGROYA flow with each new Pen (See Step 2).

Never use a bent or damaged needle.

Step 2. Check the SOGROYA flow with each new Pen

If your Pen is already in use, go to Step 3.

- Before using a new Pen, check the SOGROYA flow to make sure the growth hormone can flow through the Pen and needle.
- Turn the dose selector clockwise 1 marking on the dose counter to select 0.1 mg. You may hear a faint “click” when you turn the dose selector (See Figure E).

- 1 marking on the dose counter equals 0.1 mg (See Figure F).

- Hold the Pen with the needle pointing up. Press and hold in the dose button until the dose counter returns to “0”. The “0” must line up with the dose pointer (See Figure G).

- Check that a drop of SOGROYA appears at the needle tip (See Figure H).

If no SOGROYA appears, repeat Step 2 up to 6 times.

If you still do not see a drop of SOGROYA, change the needle:

- Carefully remove the needle from the Pen by turning the needle counterclockwise. Place the needle in a sharps disposal container immediately (See Step 5).
- Repeat Step 2 again.

Do not use the Pen if a drop of SOGROYA still does not appear after changing the needle and repeating Step 2. Call Novo Nordisk at 1-888-668-6444 for help.

Step 3. Select your dose

- To start, check that the dose pointer is set at “0”.
- Turn the dose selector clockwise to select the dose you need (See Figure I). When you have selected your dose, you can go to Step 4.

If there is not enough SOGROYA left to select a full dose, see Frequently Asked Questions.

The dose counter shows the dose in “mg” (See Figure J and Figure K). Always use the dose counter to select the exact dose. Do not use the “click” sounds you hear when you turn the dose selector to select your dose. Only the dose pointer on the dose counter will show the exact dose selected.

If you select the wrong dose, you can turn the dose selector clockwise or counterclockwise to the correct dose (See Figure L).

The Pen “clicks” sound and feel differently when the dose selector is turned clockwise, counterclockwise, or if you forcefully move it past the number of “mg” left in the Pen.

Step 4. Inject your dose

- Select the injection site.
- SOGROYA can be injected under the skin (subcutaneously) of your stomach area (abdomen), upper arms, upper legs (thighs) or buttocks as instructed by your healthcare provider (See Figure M). Change the injection site every week.
- Wipe the injection site with an alcohol pad and let the area dry.
- Insert the needle into your skin as your healthcare provider has shown you (See Figure N).
- Make sure you can see the dose counter. Do not cover it with your fingers. This could block the injection.

- Press and hold down the dose button until the dose counter shows “0” (See Figure O). The “0” must line up with the dose pointer. You may then hear or feel a “click”.
- Continue to hold down the dose button with the needle in your skin.

If “0” does not appear in the dose

counter after continuously pressing the dose button, your needle may be blocked or damaged. See Frequently Asked Questions.

Keep holding down the dose button with the needle in your skinand slowly count to 6 to make sure that the full dose has been delivered (See Figure P).

- Carefully remove the needle from your skin (See Figure Q). If blood appears at the injection site, press lightly with a gauze pad. Do not rub the area.

You may see a drop of SOGROYA at the needle tip after injecting. This is normal and does not affect your dose.

Step 5. After your injection

- Carefully remove the needle from the Pen by turning the needle counterclockwise (See Figure R).
- Place the needle in an FDA-cleared sharps disposal container immediately to reduce the risk of a needle stick (See Figure R).

Always throw away (dispose of) the needle after each injection.

For further information about safe sharps disposal, see Frequently Asked Questions.

- Put the Pen cap on your Pen after each use to protect SOGROYA from direct light (See Figure S).
See “How should I store my SOGROYA Pen?”.

Do not try to put the needle cap back on. You may stick yourself with the needle.

Always remove the needle from your Pen immediately after each injection. This reduces the risk of contamination, infection, leakage of SOGROYA, and blocked needles leading to incorrect dosing.

How should I store my SOGROYA Pen?

                        Before you use SOGROYA Pen for the first time:
- Store your new, unused SOGROYA Pen in a refrigerator between 36°F to 46°F (2°C to 8°C).
- Store your new, unused SOGROYA Pen with the cap on and in the original carton.
- Do not freeze SOGROYA.
- When stored in the refrigerator, do not store the SOGROYA Pen directly next to the cooling element.
- Keep SOGROYA away from direct heat and light.
- Do not use SOGROYA if it has been frozen or in temperatures warmer than 86ºF (30°C).
- Do not use SOGROYA after the expiration date printed on the carton and the Pen.
                        After you use SOGROYA Pen and there is still medicine left:
- Store remaining SOGROYA in the refrigerator between 36°F to 46°F (2°C to 8°C) and use within 6 weeks.
- Store your in-use SOGROYA Pen with the cap on and keep it in the original carton.

Do not store SOGROYA Pen with the needle attached.

If needed, unused and in-use SOGROYA pens can be stored out of the refrigerator. SOGROYA pens can be stored at room temperature no warmer than 77ºF (25ºC) for up to 3 days (72 hours) and then returned to the refrigerator. Throw away (dispose of) SOGROYA if it has been stored above 77°F (25°C) for more than 3 days (72 hours) or in temperatures warmer than 86°F (30°C).

Always keep your SOGROYA Pen and needles out of reach of others, especially children.

Frequently Asked Questions

How do I see how much SOGROYA is left in my Pen?

The Pen scale shows you approximately how much SOGROYA is left in your Pen (See Figure T).

To see how much SOGROYA is left in your Pen, use the dose counter:

Turn the dose selector clockwise until the dose counter stops. The dose pointer will line up with the number of “mg” left in the Pen. You can select a maximum dose of 8.0 mg. If the dose counter stops with the dose pointer lined up with “8”, at least 8.0 mg are left in your Pen.

If the dose counter stops with the dose pointer lined up with “4.8”, only 4.8 mg are left in your Pen (See Figure U).

What if I need a larger dose than what is left in my Pen?

It is not possible to select a larger dose on the dose counter than the number of “mg” left in your Pen. If you need more SOGROYA than you have left in your Pen, you can use a new Pen or split your dose between your current Pen and a new Pen. Only split your dose if you have been trained or advised by your healthcare provider on how to do this. You may find it helpful to use a calculator to plan the doses as instructed by your healthcare provider.

Be very careful to calculate your split dose correctly so that you do not give the wrong dose. If you are not sure how to split your dose using 2 Pens, then select and inject the dose you need with a new Pen.

What if no SOGROYA appears when I check the flow?

A. Your needle may be blocked or damaged, if no SOGROYA appears at the needle tip. Remove the needle as described in Step 5 and repeat Step 1 and Step 2.

B. Your Pen may be defective, if SOGROYA still does not appear after changing the needle. Do not use the Pen. Contact Novo Nordisk at 1-888-668-6444.

What if “0” does not appear after completing my injection?

The needle may be blocked or damaged, and you have not received any SOGROYA,even though the dose counter has moved from the dose that you have set. Remove the needle as described in Step 5 and repeat Step 1 to Step 4.

How should I take care of my Pen?

Be careful not to drop your Pen or knock it against hard surfaces. Do not expose your Pen to dust, dirt, liquid, or direct light. See “How should I store SOGROYA?” Do not try to refill your Pen, it is prefilled.

What if I drop my Pen?

If you drop your Pen or think that something is wrong with it, attach a new disposable needle and check the SOGROYA flow before you inject (See Step 1 and Step 2). Do not try to repair your Pen or pull it apart.

How do I clean my Pen?

Do not wash, soak, or lubricate your Pen. If necessary, clean it with mild detergent on a moistened cloth.

Frequently Asked Questions

How do I throw away (dispose of) used SOGROYAneedles and Pens?

Put your used needles and Pens in an FDA-cleared sharps disposal container right away after use. Do not throw away (dispose of) loose needles and Pens in your household trash. If you do not have an FDA-cleared sharps disposal container, you may use a household container that is:

- made of a heavy-duty plastic,
- can be closed with a tight-fitting, puncture-resistant lid, without sharps being able to come out,
- upright and stable during use,
- leak-resistant, and
- properly labeled to warn of hazardous waste inside the container.

When your sharps disposal container is almost full, you will need to follow your community guidelines for the right way to dispose of your sharps disposal container. There may be state or local laws about how you should dispose of used needles and Pens. For more information about safe sharps disposal, and for specific information about safe sharps disposal in the state that you live in, go to the FDA’s website at:

http://www.fda.gov/safesharpsdisposal.

Do not dispose of your used sharps disposal container in your household trash unless your community guidelines permit this. Do not recycle your used sharps disposal container.

Important information

- Caregivers must be very careful when handling needles to reduce the risk of needle sticks and infection.

www.sogroya.com

PATENT Information: http://novonordisk-us.com/products/product-patents.html

SOGROYA® is a registered trademark of Novo Nordisk Health Care AG.

Novo Nordisk® is a registered trademark of Novo Nordisk A/S.

© 2004-2023 Novo Nordisk Health Care AG

For further information contact:

Novo Nordisk Inc.

800 Scudders Mill Road

Plainsboro, NJ 08536, USA

1-888-668-6444

Sogroya.com

Manufactured by:

Novo Nordisk Inc.

Plainsboro, NJ 08536

U.S. License No. 1261

This Instructions for Use has been approved by the U.S. Food and Drug Administration.

Issued: 4/2023

Version: 1

Instructions for Use – Norditropin® and Sogroya® with PenMate®

INSTRUCTIONS FOR USE

Norditropin® (nor-dee-tro-pin) FlexPro®

(somatropin)

injection

prefilled pen with PenMate®

and

Sogroya® (suh-GROY-uh)

(somapacitan-beco)

injection

prefilled pen with PenMate®

Read this Instructions for Use before you start using your Pen with PenMate.

- PenMate hides the needle when you inject your Norditropin growth hormone with Norditropin FlexPro 5 mg/1.5 mL, 10 mg/1.5 mL, and 15 mg/1.5 mL Pens or Sogroya growth hormone with Sogroya 5 mg/1.5 mL, 10 mg/1.5 mL, and 15 mg/1.5 mL Pens, so that you cannot see the needle.
- Use your PenMate only after you have been trained by a healthcare provider.
- People who are blind or have poor eyesight should only use the PenMate and Pen with help from a person with good eyesight who is trained to use the PenMate and Pen.
- The figures in this Instructions for Use show PenMate being used with a Norditropin FlexPro 5 mg/1.5 mL Pen and a NovoFine needle that is 8 mm long. Even if you are using a Norditropin FlexPro 10 mg/1.5 mL or 15 mg/1.5 mL Pen or a Sogroya 5 mg/1.5 mL, 10 mg/1.5 mL, or 15 mg/1.5 mL Pen or a different needle that is 8 mm long, the instructions are the same.
- Do not share your Norditropin FlexPro or Sogroya Pens and needles with another person. You may give another person an infection or get an infection from them.

Supplies you will need to use your Pen with PenMate:

- 1 PenMate. See Figure A.
- 1 Norditropin FlexPro Pen or Sogroya Pen. See Figure B. PenMate does not work with other injection devices.
- 1 disposable needle up to 8 mm long. See Figure C. Needles are not included with your PenMate or Pen.
- 2 alcohol swabs. See Figure C.
- a sharps disposal container. See Figure C. See “How should I dispose of my Pen and needles” at the end of these instructions for information on how to throw away (dispose of) used Pens and needles.

Pen:

This pen represents Norditropin FlexPro 5 mg/1.5 mL, 10 mg/1.5 mL or 15 mg/1.5 mL Pen and Sogroya 5 mg/1.5 mL, 10 mg/1.5 mL, and 15 mg/1.5 mL Pen

Needle parts and supplies:

Step 1: Preparingyour Penwith PenMate:

Wash your hands with soap and water and dry them. Check the name and the colored label on your Pen to make sure it contains the growth hormone strength prescribed by your healthcare provider.

Pull off the PenMate cap.

See Figure E.

Pull off the Pen cap and throw it away.
See Figure F.

You will not need the Pen cap with your PenMate.

Look in the Pen window. Check the liquid medicine in your Pen by turning it upside down 1 or 2 times.

See Figure G.

- Norditropin FlexPro Pen: the liquid in the Norditropin FlexPro Pen should be clear and colorless. If the liquid looks cloudy or you see particles, do not use the Norditropin FlexPro Pen.
- Sogroya Pen: the liquid in the Sogroya Pen should be clear to almost clear and colorless to slightly yellow. If the liquid looks cloudy or you see particles, do not use the Sogroya Pen.

Wipe the front stopper on the needle thread of the Pen with an alcohol swab.

See Figure H.

Insert the Pen into the PenMate. Twist the Pen clockwise until you hear or feel a click.

See Figure I.

The Pen is correctly attached in your PenMate when the display window on the Pen lines up with the insertion button on your PenMate.

Step 2. Attaching the needle to your Pen:

- Do not place a needle on your Pen until you are ready to give an injection.
- Always use a new needle for each injection.
- Do not use a bent or damaged needle.

Get a new disposable needle and tear off the paper tab.

See Figure J.

Holding the Pen with 1 hand, firmly press the needle onto the needle thread of the Pen. Screw the needle in a clockwise direction until the needle will not turn anymore.

See Figure K.

Pull off the outer needle cap and save it.

See Figure L.

You will need the outer needle cap after the injection so you can safely remove the needle from the Pen.

Pull off the inner needle cap and throw it away.
See Figure M.

A drop of liquid may appear at the needle tip. This is normal.

Step 3. Priming a new Pen:

Checking the growth hormone flow in the Pen (priming) is not needed for a Pen you have used before.

If the Pen has already been primed, go to Step 4.

Before you use a new Pen you must prepare it for use. Hold the Pen with 1 hand and turn the dose selector clockwise 1 marking to select the minimumdose.

See Figure N.

You may hear or feel a click when you turn the dose selector.

When you turn the dose selector 1 marking, you select the smallest amount of medicine for a dose.

See Figure O.

This lowest dose will be used for your Norditropin or Sogroya flow check dose.

Hold your Pen with PenMate with the needle pointing up. You may see air bubbles in the PenMate window. Gently tap the top of PenMate a few times to let any air bubbles rise to the top.

See Figure P.

Press the dose button until the dose pointer lines up with the “0” in the display window on the Pen and a drop of liquid appears at the needle tip.

See Figure Q.

If no drop of liquid appears at the needle tip, repeat Step 3 again up to 6 times.

If there is still no drop of liquid at the needle tip, change the needle and repeat Step 3 again.

If a drop of liquid still does not appear at the needle tip after repeating Step 3 and changing the needle, call Novo Nordisk at 1-888-668-6444 for help.

Step 4. Selecting the correct dose of Norditropin or Sogroya:

Use the dose selector on your Pen to make sure you have the exact dose selected. Your dose will be in a certain number of mg (milligrams).

To start, check that the dose pointer on the Pen is set at “0”.

Select the dose you need by turning the dose selector clockwise. If you move past your dose, turn the dose selector counterclockwise until the right number of mg lines up with the dose pointer. See Figure R.

To guide you, the dose selector click sound is different when turned clockwise (softer click) or counterclockwise (louder click). You will hear a click for every single unit dialed.

When dialing counterclockwise, be careful not to press the dose button as liquid will come out.

You can use the growth hormone scale on the side of the Pen to see about how much growth hormone is left in the Pen. You can also use the dose selector to see exactly how much growth hormone is left in the Pen.

If the Pen contains less than 2 mg, 4 mg, or 8 mg (depending on whether you use a 5 mg/1.5 mL, 10 mg/1.5 mL, or 15 mg/1.5 mL Pen), turn the dose selector until it stops. The number that lines up with the dose pointer shows how many mg are left in the Pen. You cannot set a dose higher than the number of mg left in the Pen.

If there is not enough Norditropin or Sogroya left in the Pen for your full dose, use a new Norditropin FlexPro Pen or Sogroya Pen to inject the remaining amount of your dose or contact your healthcare provider.

Remember to subtract the dose already received. For example, if the dose is 0.7 mg and you can only set the dose selector to 0.35 mg, you should inject another 0.35 mg with a new Norditropin FlexPro Pen or Sogroya Pen.

Important:

- Do not use the Pen clicks to count the number of mg you select. Only the display window and dose pointer will show the exact number.
- Do not use the growth hormone scale to measure how much liquid to inject. Only the display window and dose pointer will show the exact number.

Step 5. Selecting your injection site and injecting the dose of Norditropin or Sogroya:

Change your injection site every day. Select the injection site and wipe your skin with an alcohol swab as your healthcare provider showed you.

Norditropin or Sogroya can be injected under your skin (subcutaneously) of your buttocks, stomach area (abdomen), upper legs (thighs), upper arms, or as instructed by your healthcare provider.

See Figure S.

Hold onto both the PenMate and your Pen without touching the insertion button on the PenMate or the dose button on the Pen.

Do not press the insertion button on the PenMate before you are ready to inject your dose. This lowers the risk of hurting yourself with the needle.

Hold the PenMate firmly with 1 hand and pull the Pen out with your other hand until you hear and feel a click. See Figure T.

The needle is now hidden in PenMate.

Norditropin and Sogroya is for use under your skin only (subcutaneous). Hold the PenMate against your skin. Press the insertion button on the PenMate until you hear or feel a click.

When you hear or feel the click, the needle has been inserted automatically into your skin.

See Figure U.

You are now ready to inject your dose.

Press the dose button on the Pen to inject your dose. Do not turn the dose button while you are pressing it. If you turn the dose button, you will not inject growth hormone.

Make sure you can see the display window. Do not cover it with your fingers.

Press and hold down the dose button on the Pen until the display window returns to “0”.

The “0” must line up with the dose pointer. You may then hear or feel a firm click.

After the display window has returned to “0”, leave the needle under your skin for at least 6 seconds to make sure you get your full dose.

See Figure V.

Let go of the dose button while you wait.

See Figure V.

If the dose button cannot be pushed in completely or “0” does not appear in the display window, you did not receive the full dose. Call Novo Nordisk at 1-888-668-6444 for help. You may need a new Pen.

Important:

Always press the dose button to inject the dose. Turning the dose selector will not inject the dose.

Do not touch the display window when you inject, as this can block the injection.

Carefully lift the Pen to remove the needle from the skin.

See Figure W.

Step 6. What to do after your injection is completed:

Carefully put the outer needle cap back on the needle.

Remove the needle from the Pen after each injection.

See Figure X.

Unscrew the needle by turning it counterclockwise. Do not touch the needle. Hold the Pen with 1 hand and carefully remove the needle from the Pen with your other hand.

See Figure Y.

Throw away (dispose of) the needle. See “How should I dispose of my Pen and needles?” at the end of these instructions.

Put the PenMate cap back on your PenMate after each use to protect the growth hormone from direct light.

See Figure Z.

Important safety information to remember:

- Be careful not to drop your PenMate and Pen or knock them against a hard surface. If this happens you will need to check the growth hormone flow.
- Donot try to put the inner needle cap back on the needle. You may stick yourself with the needle. Be careful when handling used needles to avoid needle stick injuries.
- After each use always remove and throw away (dispose of) the needle from your Pen.
- Do not share your Pen or needles with other people.
- If your PenMate is damaged or lost, you can still use your Pen without your PenMate.
- Always keep your Pen and needles out of reach of others, especially children.

How should I replace an empty Pen?

PenMate is reusable and should not be thrown away (disposed of). Reuse your PenMate by replacing your Pen when it is empty.

When your Pen is empty, twist the Pen counterclockwiseuntil you hear or feel a click.

See Figure AA.

Gently pull the Pen out of PenMate.

See Figure BB.

Before throwing away (disposing of) your empty Pen, make sure the needle has been removed. See “How should I dispose of my Pen and needles?” at the end of these instructions.

Insert the new Pen into your PenMate.

See Figure CC.

Twist the Pen clockwise until you hear or feel a click.

See Figure DD.

The Pen is correctly attached in your PenMate when the display window on the Pen lines up with the insertion button on your PenMate.

How should I store my PenMate and Pen?

- Do not expose your PenMate or Pen to dust, dirt, liquid, or direct light.
- Store your PenMate and Pen in their case. See Figure D at the beginning of these instructions.
- When your Pen is inserted in PenMate, store it as described in the Patient Information leaflet that comes with your Pen.

How should I care for and clean my Pen with PenMate?

- Do not try to refill your Pen. It is prefilled.
- Do not try to repair your PenMate or your Pen.
- Only clean your PenMate or Pen with a mild detergent on a moistened cloth.
- Do not wash, soak, or lubricate your PenMate or Pen. Do not use products containing bleaching agents, such as chlorine, iodine, or alcohol to clean your PenMate or Pen. These products may damage them.
- If there is liquid growth hormone on the outside of your PenMate or Pen, clean it with a mild detergent on a moistened cloth before it dries up.

How should I throw away (dispose of) my Pen and needles?

- Put your used needles and Pens in a FDA-cleared sharps disposal container right away after use. Do not throw away (dispose of) loose needles and Pens in your household trash.
- If you do not have a FDA-cleared sharps disposal container, you may use a household container that is:
  - made of a heavy-duty plastic,
  - can be closed with a tight-fitting, puncture-resistant lid, without sharps being able to come out,
  - upright and stable during use,
  - leak-resistant, and
  - properly labeled to warn of hazardous waste inside the container.
- When your sharps disposal container is almost full, you will need to follow your community guidelines for the right way to dispose of your sharps disposal container. There may be state or local laws about how you should throw away used needles and Pens. For more information about safe sharps disposal, and for specific information about sharps disposal in the state that you live in, go to the FDA’s website at: http://www.fda.gov/safesharpsdisposal.
- Do not dispose of your used sharps disposal container in your household trash unless your community guidelines permit this. Do not recycle your used sharps disposal container.

Need help?

PenMate must only be used according to the instructions provided. The manufacturer cannot be held responsible for any problems with PenMate if these instructions have not been followed.

If you find that your PenMate or case is defective, make sure to have Novo Nordisk replace it. Call the number below to order a new PenMate or case and arrange return of the defective item for inspection.

For help or further information, write to:

Novo Nordisk Inc.

800 Scudders Mill Road

Plainsboro, NJ 08536, USA

Visit norditropin.com or sogroya.com

Or call: 1-888-668-6444

PATENT Information: http://novonordisk-us.com/products/product-patents.html

Novo Nordisk®, PenMate® and NovoFine® are registered trademarks of Novo Nordisk A/S

Norditropin®, Sogroya® and FlexPro® are registered trademarks of Novo Nordisk Health Care AG.

© 2025 Novo Nordisk A/S

Manufactured by:

Novo Nordisk A/S

Novo Allé

DK-2880 Bagsvaerd

Denmark

This Instructions for Use has been approved by the U.S. Food and Drug Administration.

Issued: 01/2025

PRINCIPAL DISPLAY PANEL – 5 mg

Sogroya® 5 mg pen NDC 0169-2035-11
(somapacitan-beco) injection List: 203511

5 mg / 1.5 mL (3.3 mg/mL) Prefilled Pen

For subcutaneous Use Only

1x1.5 mL single-patient use prefilled pen

Dials in 0.025 mg increments and contains 5 mg total

Rx only

once weekly

PRINCIPAL DISPLAY PANEL – 10 mg

Sogroya® 10 mg pen NDC 0169-2030-11
(somapacitan-beco) injection List: 203011

10 mg / 1.5 mL (6.7 mg/mL) Prefilled Pen

For subcutaneous Use Only

1x1.5 mL single-patient use prefilled pen

Dials in 0.05 mg increments and contains 10 mg total

Rx only

once weekly

PRINCIPAL DISPLAY PANEL – 15 mg

Sogroya® 15 mg pen NDC 0169-2037-11
(somapacitan-beco) injection List: 203711

15 mg / 1.5 mL (10 mg/mL) Prefilled Pen

For subcutaneous Use Only

1x1.5 mL single-patient use prefilled pen

Dials in 0.1 mg increments and contains 15 mg total

Rx only

once weekly